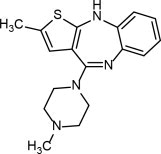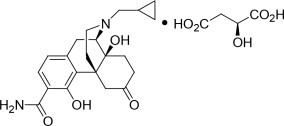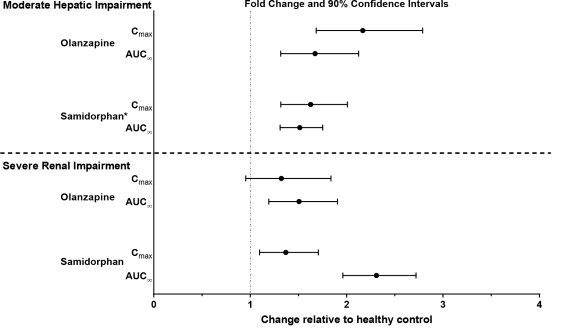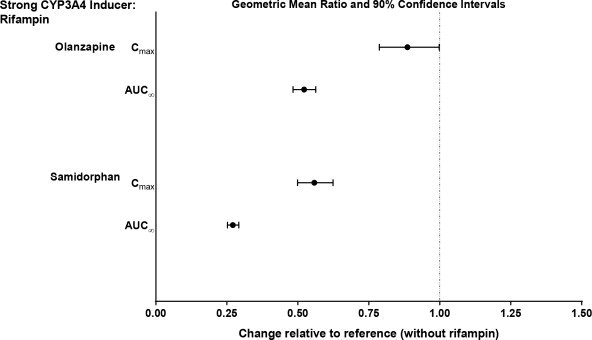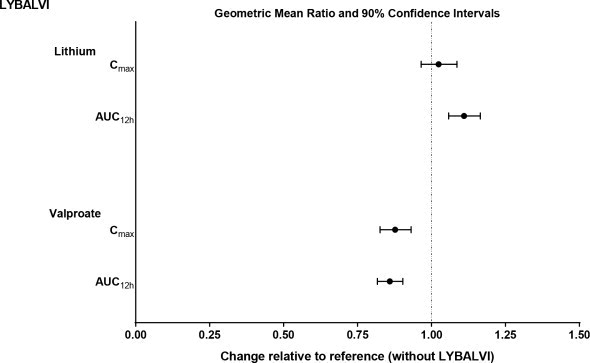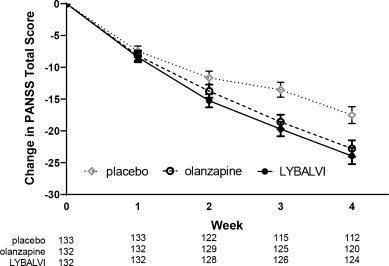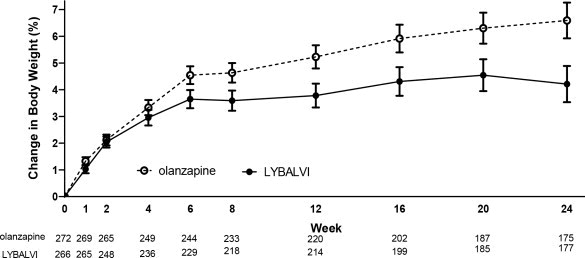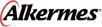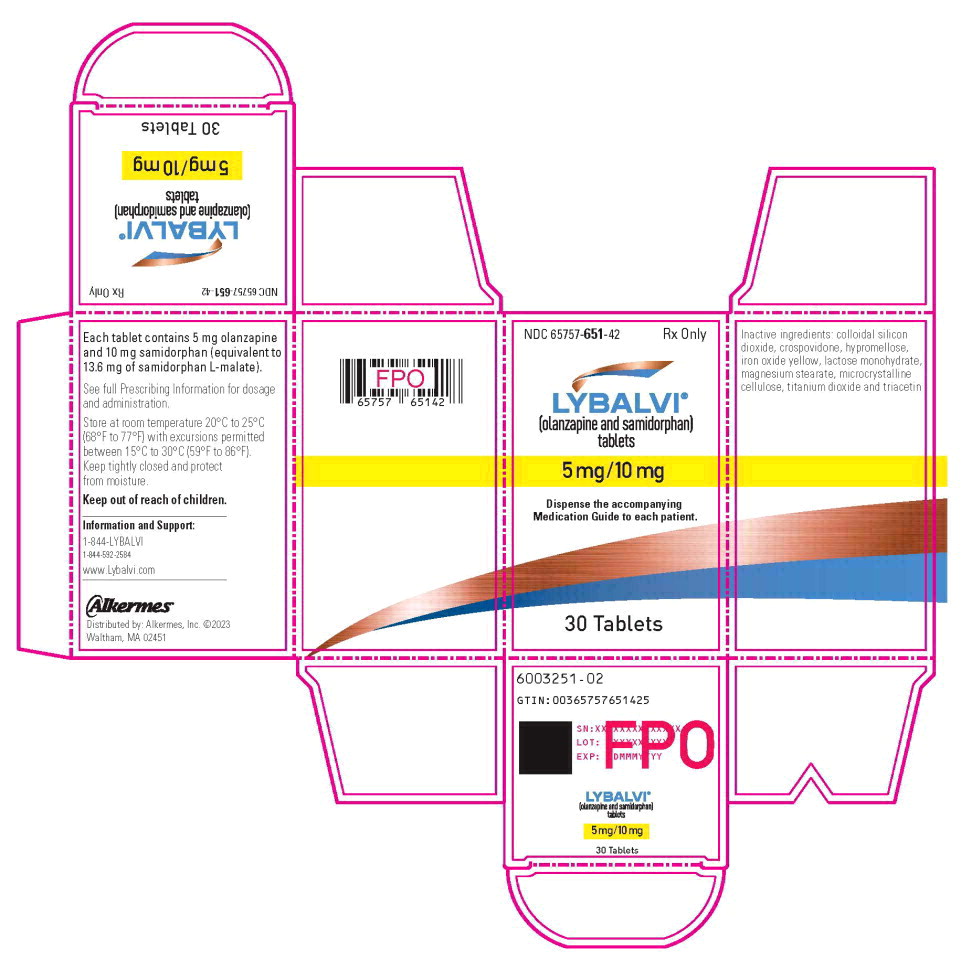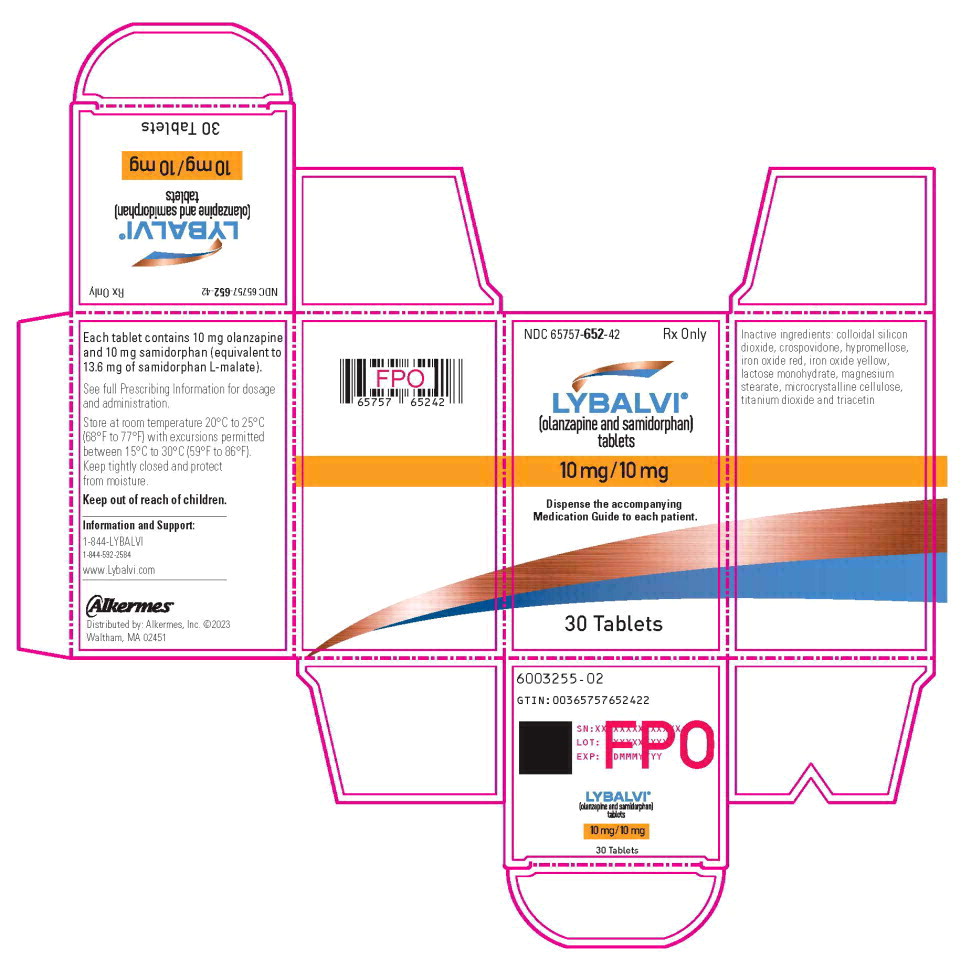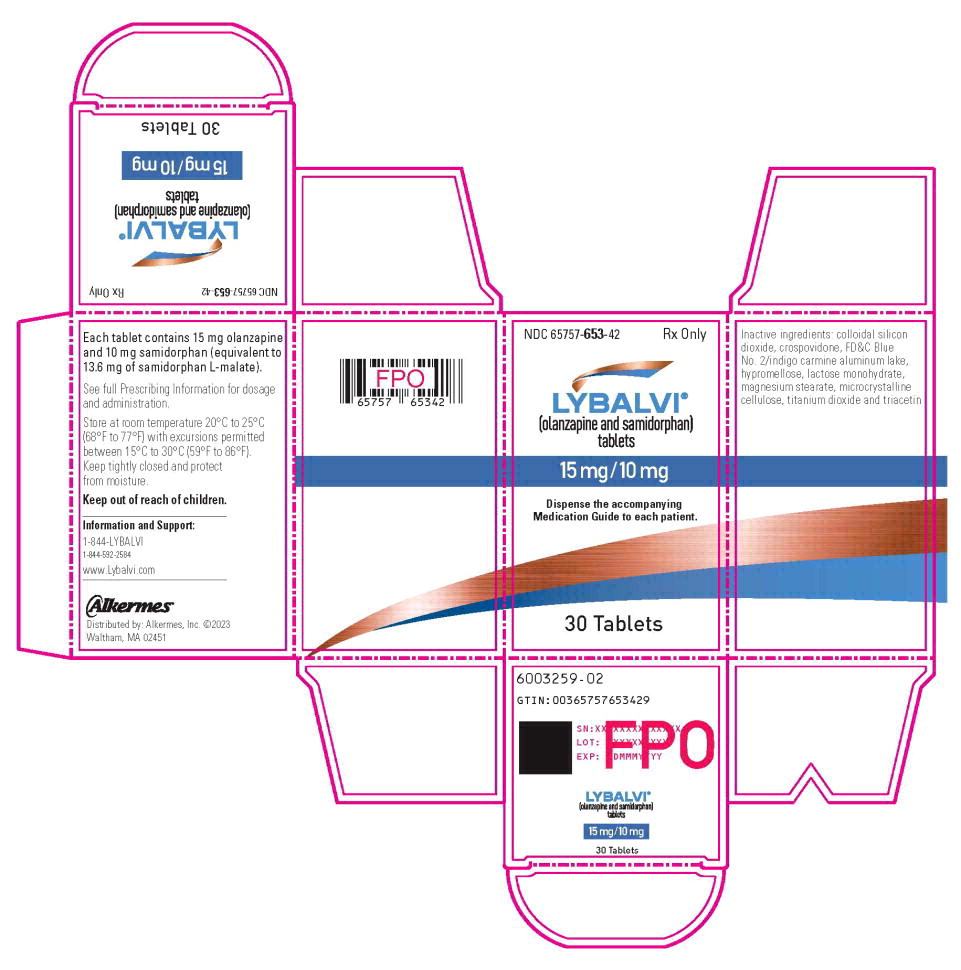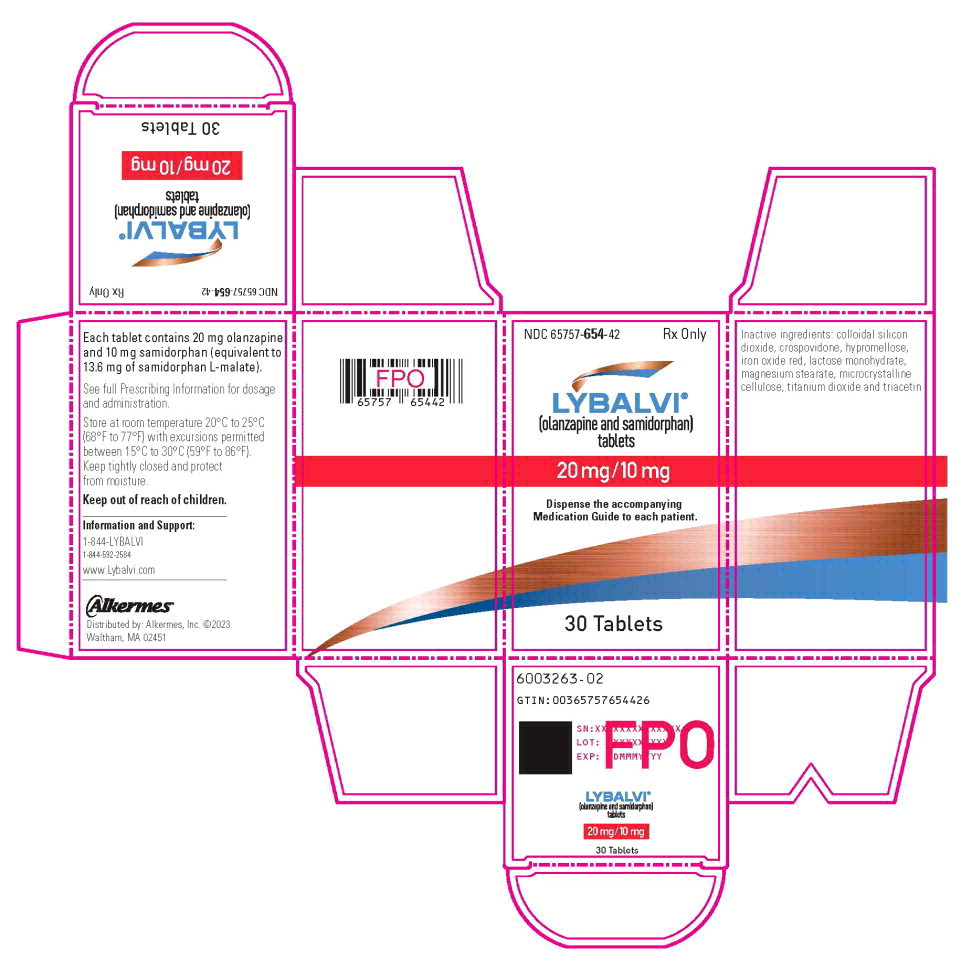 DRUG LABEL: LYBALVI
NDC: 65757-651 | Form: TABLET, FILM COATED
Manufacturer: Alkermes, Inc.
Category: prescription | Type: HUMAN PRESCRIPTION DRUG LABEL
Date: 20260131

ACTIVE INGREDIENTS: olanzapine 5 mg/1 1; samidorphan L-malate 10 mg/1 1
INACTIVE INGREDIENTS: lactose monohydrate; microcrystalline cellulose; crospovidone; magnesium stearate; silicon dioxide; hypromellose, unspecified; titanium dioxide; triacetin; ferric oxide yellow

HIGHLIGHTS OF PRESCRIBING INFORMATION

These highlights do not include all the information needed to use LYBALVI® safely and effectively. See full prescribing information for LYBALVI®.
LYBALVI® (olanzapine and samidorphan) tablets, for oral use
Initial U.S. Approval: 2021

WARNING: INCREASED MORTALITY IN ELDERLY PATIENTS WITH DEMENTIA-RELATED PSYCHOSIS

See full prescribing information for complete boxed warning.

Elderly patients with dementia-related psychosis treated with antipsychotic drugs are at an increased risk of death. LYBALVI is not approved for the treatment of patients with dementia-related psychosis. (5.1)

1 INDICATIONS AND USAGE

LYBALVI is a combination of olanzapine, an atypical antipsychotic, and samidorphan, an opioid antagonist, indicated for the treatment of:

- Schizophrenia in adults (1)
- Bipolar I disorder in adults (1)
  - Acute treatment of manic or mixed episodes as monotherapy and as adjunct to lithium or valproate
  - Maintenance monotherapy treatment

2 DOSAGE AND ADMINISTRATION

Indication | Recommended Starting Dose (olanzapine/samidorphan) | Recommended Dose (olanzapine/samidorphan)
Schizophrenia (2.2) | 5 mg/10 mg or 10 mg/10 mg | 10 mg/10 mg 15 mg/10 mg 20 mg/10 mg
Bipolar I disorder (manic or mixed episodes) (2.3) | 10 mg/10 mg or 15 mg/10 mg | 5 mg/10 mg 10 mg/10 mg 15 mg/10 mg 20 mg/10 mg
Bipolar I disorder adjunct to lithium or valproate (2.3) | 10 mg/10 mg | 10 mg/10 mg 15 mg/10 mg 20 mg/10 mg

- See the full prescribing information for the recommended titration and maximum recommended dosage. (2.2, 2.3)
- Administer LYBALVI once daily with or without food. Do not divide tablets or combine strengths. (2.4)
- Recommended starting dosage is 5 mg/10 mg once daily in patients who have a predisposition to hypotensive reactions, have potential for slower metabolism of olanzapine, or may be more pharmacodynamically sensitive to olanzapine. (2.5)

3 DOSAGE FORMS AND STRENGTHS

Tablets (olanzapine/samidorphan): 5 mg/10 mg, 10 mg/10 mg, 15 mg/10 mg and 20 mg/10 mg. (3)

4 CONTRAINDICATIONS

- Patients using opioids. (4)
- Patients undergoing acute opioid withdrawal. (4)
- If LYBALVI is administered with lithium or valproate, refer to the lithium or valproate Prescribing Information for the contraindications for those products. (4)

5 WARNINGS AND PRECAUTIONS

- Cerebrovascular Adverse Reactions in Elderly Patients with Dementia-Related Psychosis: Increased incidence of cerebrovascular adverse reactions (e.g., stroke, transient ischemic attack, including fatalities). (5.2)
- Precipitation of Opioid Withdrawal in Patients Who are Dependent on Opioids: LYBALVI can precipitate opioid withdrawal in patients who are dependent on opioids. Prior to initiating LYBALVI, there should be at least a 7-day opioid-free interval from the last use of short-acting opioids, and at least a 14-day opioid-free interval from the last use of long-acting opioids to avoid precipitation of opioid withdrawal. (2.1, 5.3)
- Vulnerability to Life-Threatening Opioid Overdose:
  - Risk of Opioid Overdose from Attempts to Overcome LYBALVI Opioid Blockade: Attempts to overcome LYBALVI opioid blockade with high or repeated doses of opioids may lead to fatal opioid intoxication, particularly if LYBALVI therapy is interrupted or discontinued. (5.4)
  - Risk of Resuming Opioids in Patients with Prior Opioid Use: Patients with a history of chronic opioid use prior to LYBALVI treatment may have decreased opioid tolerance if LYBALVI therapy is interrupted or discontinued. (5.4)
- Neuroleptic Malignant Syndrome: Manage with immediate discontinuation and close monitoring. (5.5)
- Drug Reaction with Eosinophilia and Systemic Symptoms (DRESS): Discontinue if DRESS is suspected. (5.6)
- Metabolic Changes: Monitor for hyperglycemia/diabetes mellitus, dyslipidemia, and weight gain. (5.7)
- Tardive Dyskinesia: Discontinue if clinically appropriate. (5.8)
- Orthostatic Hypotension and Syncope: Monitor heart rate and blood pressure and warn patients with known cardiovascular or cerebrovascular disease, and risk of dehydration or syncope. (5.9)
- Leukopenia, Neutropenia, and Agranulocytosis: Perform complete blood counts in patients with a history of a clinically significant low white blood cell (WBC) count. Consider discontinuation if clinically significant decline in WBC in the absence of other causative factors. (5.11)
- Seizures: Use cautiously in patients with a history of seizures or with conditions that lower the seizure threshold. (5.13)
- Potential for Cognitive and Motor Impairment: Use caution when operating machinery. (5.14)
- Anticholinergic (Antimuscarinic) Effects: Use with caution with other anticholinergic drugs and in patients with urinary retention, prostatic hypertrophy, constipation, paralytic ileus or related conditions. (5.16)
- Hyperprolactinemia: May elevate prolactin levels. (5.17)

6 ADVERSE REACTIONS

Most common adverse reactions (incidence ≥5% and at least twice placebo):

- Schizophrenia (LYBALVI): weight increased, somnolence, dry mouth, and headache. (6.1)
- Bipolar I Disorder, Manic or Mixed Episodes (olanzapine): somnolence, dry mouth, dizziness, asthenia, constipation, dyspepsia, increased appetite, tremor. (6.1)
- Bipolar I Disorder, Manic or Mixed Episodes, adjunct to Lithium or Valproate (olanzapine): dry mouth, weight gain, increased appetite, dizziness, back pain, constipation, speech disorder, increased salivation, amnesia, paresthesia. (6.1)

To report SUSPECTED ADVERSE REACTIONS, contact Alkermes at 1-888-235-8008 or FDA at 1-800-FDA-1088 or www.fda.gov/medwatch.

7 DRUG INTERACTIONS

- Strong CYP3A4 Inducers: Not recommended. (7.1)
- Strong CYP1A2 Inhibitors: Consider dosage reduction of olanzapine component of LYBALVI. (7.1)
- CYP1A2 Inducer: Consider dosage increase of the olanzapine component of LYBALVI. (7.1)
- CNS Acting Drugs: May potentiate orthostatic hypotension. (7.1)
- Anticholinergic Drugs: Can increase risk for severe gastrointestinal adverse reactions. (7.1)
- Antihypertensive Agents: Monitor blood pressure. (7.2)
- Levodopa and Dopamine Agonists: Not recommended. (7.2)

8 USE IN SPECIFIC POPULATIONS

- Pregnancy: May cause extrapyramidal and/or withdrawal symptoms in neonates with third trimester exposure. (8.1)
- Renal Impairment: Use is not recommended in patients with end-stage renal disease. (8.7)

FULL PRESCRIBING INFORMATION

WARNING: INCREASED MORTALITY IN ELDERLY PATIENTS WITH DEMENTIA-RELATED PSYCHOSIS

Elderly patients with dementia-related psychosis treated with antipsychotic drugs are at an increased risk of death. LYBALVI is not approved for the treatment of patients with dementia-related psychosis [see Warnings and Precautions (5.1)].

1 INDICATIONS AND USAGE

LYBALVI is indicated for the treatment of:

- Schizophrenia in adults
- Bipolar I disorder in adults
  - Acute treatment of manic or mixed episodes as monotherapy and as adjunct to lithium or valproate
  - Maintenance monotherapy treatment

2 DOSAGE AND ADMINISTRATION

2.1 LYBALVI Initiation In Patients Using Opioids

LYBALVI is contraindicated in patients using opioids or undergoing acute opioid withdrawal.

In patients who use opioids, delay initiation of LYBALVI for a minimum of 7 days after last use of short-acting opioids and 14 days after last use of long-acting opioids [see Warnings and Precautions (5.3)].

2.2 Recommended Dosage in Schizophrenia

Initiate LYBALVI at 5 mg/10 mg (contains 5 mg of olanzapine and 10 mg of samidorphan) or 10 mg/10 mg (contains 10 mg of olanzapine and 10 mg of samidorphan) orally once daily. The recommended dosage is 10 mg/10 mg, 15 mg/10 mg (contains 15 mg of olanzapine and 10 mg of samidorphan), or 20 mg/10 mg (contains 20 mg of olanzapine and 10 mg of samidorphan) once daily.

Dosage may be adjusted at weekly intervals of 5 mg (based on the olanzapine component of LYBALVI) depending upon clinical response and tolerability, up to the maximum recommended dosage of 20 mg/10 mg once daily.

2.3 Recommended Dosage in Bipolar I Disorder (Manic or Mixed Episodes)

Monotherapy: Initiate LYBALVI at 10 mg/10 mg or 15 mg/10 mg once daily. The recommended dosage is 10 mg/10 mg, 15 mg/10 mg, or 20 mg/10 mg once daily. The maximum recommended dosage is 20 mg/10 mg once daily.

Dosage adjustments should occur at intervals of not less than 24 hours. When dosage adjustments are necessary, dose increments/decrements of 5 mg (based on the olanzapine component of LYBALVI) are recommended.

Maintenance Monotherapy: Administer LYBALVI at 5 mg/10 mg, 10 mg/10 mg, 15 mg/10 mg, or 20 mg/10 mg once daily.

Adjunctive to lithium or valproate: Initiate LYBALVI at 10 mg/10 mg once daily. The recommended dosage is 10 mg/10 mg, 15 mg/10 mg or 20 mg/10 mg, once daily.

Dosage may be adjusted at weekly intervals of 5 mg (based on the olanzapine component of LYBALVI), depending upon clinical response and tolerability, up to the maximum recommended dosage of 20 mg/10 mg once daily.

2.4 Administration Information

Administer LYBALVI orally once daily with or without food as a single tablet.

Do not divide tablets or combine strengths.

2.5 Dosage Recommendations in Specific Populations

The recommended starting dosage of LYBALVI is 5 mg/10 mg once daily in patients who have a higher risk of hypotensive reactions, are at risk of slower olanzapine metabolism, or may be more pharmacodynamically sensitive to olanzapine [see Warnings and Precautions (5.9), Drug Interactions (7.2), Use in Specific Populations (8.5), and Clinical Pharmacology (12.3)]. If dose escalation is necessary, increase the dosage slowly in these patients.

3 DOSAGE FORMS AND STRENGTHS

LYBALVI tablets are available in four strengths (Table 1).

Table 1: LYBALVI Tablet Strengths and Identifying Features
Tablet Strength | Tablet Color/Shape | Tablet Markings
5 mg/10 mg (olanzapine/samidorphan) | Yellow, capsule-shaped | “OS” and “5”
10 mg/10 mg (olanzapine/samidorphan) | Orange, capsule-shaped | “OS” and “10”
15 mg/10 mg (olanzapine/samidorphan) | Blue, capsule-shaped | “OS” and “15”
20 mg/10 mg (olanzapine/samidorphan) | Pink, capsule-shaped | “OS” and “20”

4 CONTRAINDICATIONS

LYBALVI is contraindicated in patients:

- who are using opioids [see Warnings and Precautions (5.3, 5.4), Drug Interactions (7.3)].
- who are undergoing acute opioid withdrawal [see Warnings and Precautions (5.3, 5.4), Drug Interactions (7.3)].

If LYBALVI is administered with lithium or valproate, refer to the lithium or valproate Prescribing Information for the contraindications for these products [see Warnings and Precautions (5.18)].

5 WARNINGS AND PRECAUTIONS

5.1 Increased Mortality in Elderly Patients with Dementia-Related Psychosis

Elderly patients with dementia-related psychosis treated with antipsychotic drugs are at an increased risk of death. In placebo-controlled clinical trials of elderly patients with dementia-related psychosis, the incidence of death in olanzapine-treated patients was significantly greater than in placebo-treated patients (3.5% vs 1.5%, respectively). Analyses of 17 placebo-controlled trials (modal duration of 10 weeks), largely in patients taking atypical antipsychotic drugs, revealed a risk of death in the drug-treated patients of between 1.6 to 1.7 times that seen in placebo-treated patients. Over the course of a typical 10-week controlled trial, the rate of death in drug-treated patients was about 4.5%, compared to a rate of about 2.6% in the placebo group. Although the causes of death were varied, most of the deaths appeared to be either cardiovascular (e.g., heart failure, sudden death) or infectious (e.g., pneumonia) in nature. LYBALVI is not approved for the treatment of patients with dementia-related psychosis [see Warnings and Precautions (5.2)].

5.2 Cerebrovascular Adverse Reactions, Including Stroke in Elderly Patients with Dementia-Related Psychosis

Cerebrovascular adverse reactions (e.g., stroke, transient ischemic attack), including fatalities, were reported in patients in trials of olanzapine in elderly patients with dementia-related psychosis. In placebo-controlled trials, there was a significantly higher incidence of cerebrovascular adverse reactions in patients treated with olanzapine compared to patients treated with placebo. LYBALVI is not approved for the treatment of patients with dementia-related psychosis [see Warnings and Precautions (5.1)].

5.3 Precipitation of Severe Opioid Withdrawal in Patients Who Are Physiologically Dependent on Opioids

Samidorphan, an opioid antagonist that is a component of LYBALVI, can precipitate opioid withdrawal in patients who are dependent on opioids, which can lead to an opioid withdrawal syndrome, sometimes requiring hospitalization. Therefore, LYBALVI is contraindicated in patients who are using opioids or undergoing acute opioid withdrawal. Prior to initiating LYBALVI, there should be at least a 7-day opioid-free interval from last use of short-acting opioids, and at least a 14-day opioid-free interval from the last use of long-acting opioids. Explain the risks associated with precipitated withdrawal and the importance of giving an accurate account of last opioid use to patients and caregivers [see Dosage and Administration (2.1), Drug Interactions (7.3)].

5.4 Vulnerability to Life-Threatening Opioid Overdose

Risk of Opioid Overdose from Attempts to Overcome Samidorphan Blockade

LYBALVI contains samidorphan, an opioid antagonist. Attempting to overcome LYBALVI's opioid blockade with high or repeated doses of exogenous opioids (e.g., because of ineffective analgesia or opioid withdrawal symptoms) could lead to life-threatening or fatal opioid intoxication (e.g., respiratory arrest, circulatory collapse), particularly if LYBALVI therapy is interrupted or discontinued, subjecting the patient to high levels of unopposed opioid agonist as the samidorphan blockade wanes. Inform patients of the potential consequences of trying to overcome the opioid blockade and the serious risks of taking opioids concurrently with LYBALVI or while transitioning off LYBALVI.

In emergency situations, if a LYBALVI-treated patient requires opioid treatment as part of anesthesia or analgesia:

- Discontinue LYBALVI,
- Opioids should be administered by individual(s) trained in the use of anesthetic drugs and the management of the respiratory effects of opioids, specifically the establishment and maintenance of a patent airway and assisted ventilation, and
- Appropriately trained personnel should continuously monitor the patient in a setting equipped and staffed for cardiopulmonary resuscitation.

For recommendations on starting opioids in LYBALVI-treated patients in non-emergent situations, see Drug Interactions (7.3).

Risk of Resuming Opioids in Patients with Prior Opioid Use

Patients with a history of chronic opioid use prior to treatment with LYBALVI may have decreased opioid tolerance if LYBALVI therapy is interrupted or discontinued. Advise patients that this decreased tolerance may increase the risk of opioid overdose if opioids are resumed at the previously tolerated dosage.

5.5 Neuroleptic Malignant Syndrome

Neuroleptic Malignant Syndrome (NMS), a potentially fatal symptom complex, has been reported in association with administration of antipsychotic drugs. Clinical manifestations of NMS are hyperpyrexia, muscle rigidity, delirium, and autonomic instability. Additional signs may include elevated creatine phosphokinase, myoglobinuria (rhabdomyolysis), and acute renal failure.

If NMS is suspected, immediately discontinue LYBALVI and provide intensive symptomatic treatment and monitoring.

5.6 Drug Reaction with Eosinophilia and Systemic Symptoms

Drug Reaction with Eosinophilia and Systemic Symptoms (DRESS) has been reported with exposure to olanzapine, a component of LYBALVI [see Adverse Reactions (6.2)]. DRESS may present with a cutaneous reaction (such as rash or exfoliative dermatitis), eosinophilia, fever, and/or lymphadenopathy with systemic complications such as hepatitis, nephritis, pneumonitis, myocarditis, and/or pericarditis. DRESS is sometimes fatal. Discontinue LYBALVI if DRESS is suspected.

5.7 Metabolic Changes

Atypical antipsychotic drugs, including LYBALVI, have been associated with metabolic changes that include hyperglycemia, diabetes mellitus, dyslipidemia, and body weight gain [see Adverse Reactions (6.1)]. While all drugs in the class have been shown to produce some metabolic changes, each drug has its own specific risk profile.

Hyperglycemia, in some cases extreme and associated with ketoacidosis or hyperosmolar coma or death, has been reported in patients treated with atypical antipsychotics. Any patient treated with LYBALVI should be monitored for symptoms of hyperglycemia including polydipsia, polyuria, polyphagia, and weakness. Patients who develop symptoms of hyperglycemia during treatment with LYBALVI should undergo fasting blood glucose testing. In some cases, hyperglycemia has resolved when the atypical antipsychotic was discontinued; however, some patients required anti-diabetic treatment despite discontinuation of the suspect drug. Patients starting treatment with LYBALVI should undergo fasting blood glucose testing at the beginning of treatment and periodically during treatment.

Antipsychotics have caused adverse alterations in lipids. Patients starting treatment with LYBALVI should undergo fasting lipid profile testing at the beginning of treatment and periodically during treatment.

Weight gain has been observed with use of antipsychotics. Monitor weight prior to initiating LYBALVI and frequently thereafter.

5.8 Tardive Dyskinesia

Tardive dyskinesia, a syndrome consisting of potentially irreversible, involuntary, dyskinetic movements, may develop in patients treated with antipsychotic drugs. The risk appears to be highest among the elderly, especially elderly women, but it is not possible to predict which patients are likely to develop the syndrome. Whether antipsychotic drug products differ in their potential to cause tardive dyskinesia is unknown.

The risk of developing tardive dyskinesia and the likelihood that it will become irreversible increases with the duration of treatment and the cumulative dose. The syndrome can develop after a relatively brief treatment period, even at low doses. It may also occur after discontinuation of treatment.

Tardive dyskinesia may remit, partially or completely, if antipsychotic treatment is discontinued. Antipsychotic treatment itself, however, may suppress (or partially suppress) the signs and symptoms of the syndrome, possibly masking the underlying process. The effect of symptomatic suppression on the long-term course of the syndrome is unknown.

Given these considerations, LYBALVI should be prescribed in a manner that is most likely to reduce the risk of tardive dyskinesia. Chronic antipsychotic treatment should generally be reserved for patients: 1) who suffer from a chronic illness that is known to respond to antipsychotic drugs; and 2) for whom alternative, effective, but potentially less harmful treatments are not available or appropriate. In patients who do require chronic treatment, use the lowest dose and the shortest duration of treatment producing a satisfactory clinical response should be sought. Periodically reassess the need for continued treatment.

If signs and symptoms of tardive dyskinesia appear in a patient on LYBALVI, drug discontinuation should be considered. However, some patients may require treatment with LYBALVI despite the presence of the syndrome.

5.9 Orthostatic Hypotension and Syncope

Atypical antipsychotics cause orthostatic hypotension and syncope. Generally, the risk is greatest during initial dose titration and when increasing the dose. In the 4-week, placebo-controlled study, from analysis of the vital signs data, rates of orthostatic hypotension were less than 2% in LYBALVI- and placebo-, and olanzapine-treated patients. In the 24-week, olanzapine-controlled study, from analysis of the vital signs data, rates of orthostatic hypotension in LYBALVI-treated patients were 3.7%, compared to 0.4% in olanzapine-treated patients.

Monitor orthostatic vital signs in patients who are vulnerable to hypotension (e.g., elderly patients, patients with dehydration, hypovolemia, concomitant treatment with antihypertensive medications or CNS depressants [see Drug Interactions (7.1, 7.2)], patients with known cardiovascular disease (history of myocardial infarction, ischemic heart disease, heart failure, or conduction abnormalities), and patients with cerebrovascular disease. LYBALVI has not been evaluated in patients with a recent history of myocardial infarction or unstable cardiovascular disease. Such patients were excluded from the premarketing clinical trials.

5.10 Falls

Antipsychotics, including LYBALVI, may cause somnolence, postural hypotension, motor and sensory instability, which may lead to falls and, consequently, fractures or other injuries. For patients with diseases, conditions, or medications that could exacerbate these effects, complete fall risk assessments when initiating antipsychotic treatment and recurrently for patients on long-term antipsychotic therapy.

5.11 Leukopenia, Neutropenia, and Agranulocytosis

Leukopenia and neutropenia have been reported during treatment with antipsychotic agents, including LYBALVI [see Adverse Reactions (6)]. Agranulocytosis (including fatal cases) has been reported with other agents in this class.

Possible risk factors for leukopenia and neutropenia include pre-existing low white blood cell count (WBC) or absolute neutrophil count (ANC) and history of drug-induced leukopenia or neutropenia. In patients with a pre-existing low WBC or ANC or a history of drug-induced leukopenia or neutropenia, perform a complete blood count (CBC) frequently during the first few months of therapy. In such patients, consider discontinuation of LYBALVI at the first sign of a clinically significant decline in WBC in the absence of other causative factors.

Monitor patients with clinically significant neutropenia for fever or other symptoms or signs of infection and treat promptly if such symptoms or signs occur. Discontinue LYBALVI in patients with severe neutropenia (absolute neutrophil count <1000/mm^3) and follow their WBC until recovery.

5.12 Dysphagia

Esophageal dysmotility and aspiration have been associated with antipsychotic drug use. Antipsychotic drugs, including LYBALVI, should be used cautiously in patients at risk for aspiration.

5.13 Seizures

Like other antipsychotic drugs, LYBALVI may cause seizures. This risk is greatest in patients with a history of seizures or with conditions that lower the seizure threshold. Conditions that lower the seizure threshold may be more prevalent in older patients.

5.14 Potential for Cognitive and Motor Impairment

LYBALVI, like other antipsychotics, may cause somnolence and has the potential to impair judgment, thinking, or motor skills. In a LYBALVI placebo-controlled study, somnolence occurred in 9% of LYBALVI-treated patients compared to 2.2% in patients treated with placebo.

Patients should be cautioned about operating hazardous machinery, including motor vehicles, until they are reasonably certain that LYBALVI therapy does not affect them adversely.

5.15 Body Temperature Dysregulation

Atypical antipsychotics may disrupt the body's ability to reduce core body temperature. Strenuous exercise, exposure to extreme heat, dehydration, and anticholinergic medications may contribute to an elevation in core body temperature; use LYBALVI with caution in patients who may experience these conditions.

5.16 Anticholinergic (Antimuscarinic) Effects

Olanzapine, a component of LYBALVI, exhibits in vitro muscarinic receptor affinity [see Clinical Pharmacology (12.2)]. In premarketing clinical trials with oral olanzapine, olanzapine was associated with constipation, dry mouth, and tachycardia, all adverse reactions possibly related to cholinergic antagonism. Such adverse reactions were not often the basis for discontinuations, but LYBALVI should be used with caution in patients with a current diagnosis or prior history of urinary retention, clinically significant prostatic hypertrophy, constipation, or a history of paralytic ileus or related conditions. In postmarketing experience, the risk for severe adverse reactions (including fatalities) was increased with concomitant use of anticholinergic medications [see Drug Interactions (7.1)].

5.17 Hyperprolactinemia

As with other drugs that antagonize dopamine D2 receptors, olanzapine, a component of LYBALVI, elevates prolactin levels, and the elevation can persist during chronic administration. Hyperprolactinemia may suppress hypothalamic GnRH, resulting in reduced pituitary gonadotropin secretion. This, in turn, may inhibit reproductive function by impairing gonadal steroidogenesis in both female and male patients. Galactorrhea, amenorrhea, gynecomastia, and impotence have been reported in patients receiving prolactin-elevating compounds. Long-standing hyperprolactinemia when associated with hypogonadism may lead to decreased bone density in both female and male subjects.

Tissue culture experiments indicate that approximately one-third of human breast cancers are prolactin-dependent in vitro, a factor of potential importance if the prescription of these drugs is considered in a patient with previously-detected breast cancer. As is common with compounds which increase prolactin release, an increase in mammary gland neoplasia was observed in the olanzapine carcinogenicity studies conducted in mice and rats [see Nonclinical Toxicology (13.1)]. Published epidemiologic studies have shown inconsistent results when exploring the potential association between hyperprolactinemia and breast cancer.

In the 4-week placebo-controlled trial, shifts from normal to high prolactin values (>30 ng/mL for females; >20 ng/mL for males) occurred in 41.4% of females and 32.9% of males treated with LYBALVI, in 56.1% of females and 37.1% of males treated with olanzapine, and in 10% of females and 4.8% of males treated with placebo [see Use in Specific Populations (8.3)].

In the 24-week, olanzapine-controlled study, shifts from normal to high prolactin values occurred in 32.9% of females and 22.5% of males treated with LYBALVI, and in 41.7% of females and 28.5% of males treated with olanzapine.

5.18 Risks Associated with Combination Treatment with Lithium or Valproate

If LYBALVI is administered with lithium or valproate, refer to the lithium or valproate Prescribing Information for a description of the risks for these products including, but not limited to, the warnings and precautions for lithium or valproate [see Contraindications (4)].

5.19 Interference with Laboratory Tests for Opioid Detection

LYBALVI may cause false positive results with urinary immunoassay methods used for detecting opioids. Use an alternative analytical technique (e.g., chromatographic methods) to confirm positive opioid urine drug screen results [see Contraindications (4) and Drug Interactions (7.4)].

6 ADVERSE REACTIONS

The following adverse reactions are discussed in detail in other sections of the labeling:

- Increased Mortality in Elderly Patients with Dementia-related Psychosis [see Boxed Warning, Warnings and Precautions (5.1)]
- Cerebrovascular Adverse Reactions, Including Stroke, in Elderly Patients with Dementia-Related Psychosis [see Warnings and Precautions (5.2)]
- Precipitation of Opioid Withdrawal in Patients Who Are Dependent on Opioids [see Warnings and Precautions (5.3)]
- Vulnerability to Life-Threatening Opioid Overdose [see Warnings and Precautions (5.4)]
- Neuroleptic Malignant Syndrome [see Warnings and Precautions (5.5)]
- Drug Reaction with Eosinophilia and Systemic Symptoms [see Warnings and Precautions (5.6)]
- Metabolic Changes [see Warnings and Precautions (5.7)]
- Tardive Dyskinesia [see Warnings and Precautions (5.8)]
- Orthostatic Hypotension and Syncope [see Warnings and Precautions (5.9)]
- Falls [see Warnings and Precautions (5.10)]
- Leukopenia, Neutropenia, and Agranulocytosis [see Warnings and Precautions (5.11)]
- Dysphagia [see Warnings and Precautions (5.12)]
- Seizures [see Warnings and Precautions (5.13)]
- Potential for Cognitive and Motor Impairment [see Warnings and Precautions (5.14)]
- Body Temperature Regulation [see Warnings and Precautions (5.15)]
- Anticholinergic (Antimuscarinic) Effects [see Warnings and Precautions (5.16)]
- Hyperprolactinemia [see Warnings and Precautions (5.17)]
- Risks Associated with Combination Treatment with Lithium or Valproate [see Warnings and Precautions (5.18)]

6.1 Clinical Studies Experience

Because clinical trials are conducted under widely varying conditions, adverse reaction rates observed in clinical trials of a drug cannot be directly compared to rates in the clinical trials of another drug and may not reflect the rates observed in clinical practice.

Adverse Reactions in Patients with Schizophrenia

Patient Exposure

The safety of LYBALVI was evaluated in 1262 patients (18 to 67 years of age) diagnosed with schizophrenia in four double-blind, controlled studies and three long-term safety extension studies of up to 3 years of duration. This experience corresponds to approximately 910 person-years. In these studies, there were a total of 663 patients exposed to LYBALVI for at least 6 months, and 386 patients for at least one year.

Adverse Reactions in the Short-Term (4 week) Placebo-Controlled Trial in Adults with Schizophrenia

The most common adverse reactions (incidence of at least 5% of patients exposed to LYBALVI and greater than twice the rate of placebo) are weight increased, somnolence, dry mouth, and headache.

Adverse reactions associated with the use of LYBALVI (incidence of 2% or greater and greater than in placebo-treated patients) are shown in Table 2.

Table 2: Adverse Reactions Reported in ≥2% of LYBALVI-Treated Patients and Greater than Placebo in a 4-Week Schizophrenia Trial
Adverse Reaction | Placebo (N=134) % | LYBALVI (10 mg/10 mg, 20 mg/10 mg) (N=134) %
Weight increased | 3 | 19
Somnolence | 2 | 9
Dry mouth | 1 | 7
Headache | 3 | 6
Blood insulin increased | 1 | 3
Sedation | 0 | 2
Dizziness | 1 | 2
Neutrophil count decreased | 0 | 2

Adverse reactions that led to discontinuation in LYBALVI-treated patients in the short-term placebo-controlled trial in adults with schizophrenia include schizophrenia (1%) and abnormal liver function tests (1%).

Adverse Reactions in the Long-Term (24-week), Active-Controlled Trial in Adults with Schizophrenia

In the 24-week, olanzapine-controlled trial in patients with stable schizophrenia, adverse reactions associated with the use of LYBALVI (incidence of 2% or greater) include: weight increased (25%), somnolence (21%), dry mouth (13%), increased appetite (11%), waist circumference increased (6%), blood creatine phosphokinase increased (5%), headache (4%), lethargy (4%), sedation (4%), akathisia (3%), alanine aminotransferase increased (3%), aspartate aminotransferase increased (3%), constipation (3%), dizziness (3%), fatigue (3%), nausea (3%), blood pressure increased (3%), neutrophil count decreased (3%), blood insulin increased (2%), weight decreased (2%), and dyslipidemia (2%).

Adverse reactions that led to LYBALVI treatment discontinuation in more than one patient include somnolence (2%), weight increased (2%), neutropenia (2%), glycosylated hemoglobin increased (1%), schizophrenia (1%), and liver function test abnormal (1%).

Hyperglycemia

Mean increases in blood glucose have been observed in patients treated (median exposure of 9.2 months) with olanzapine in phase 1 of the Clinical Antipsychotic Trials of Intervention Effectiveness (CATIE). The mean increase of serum glucose (fasting and nonfasting samples) from baseline to the average of the 2 highest serum concentrations was 15.0 mg/dL. Hyperglycemia, as defined by fasting glucose ≥126 mg/dL, has been observed in patients treated with LYBALVI.

In the 4-week placebo-controlled trial in adult patients with schizophrenia, shifts in fasting glucose from normal to high occurred in 4% of patients treated with LYBALVI, 1% of patients treated with olanzapine, and no patients treated with placebo.

In the 24-week olanzapine-controlled trial, patients treated with LYBALVI were more likely to experience abnormal shifts in glycemic parameters than patients treated with olanzapine (Table 3)

Table 3: Changes in Glycemic Parameters in a 24-Week Trial of Patients with Schizophrenia
 | LYBALVI | Olanzapine
Proportion of Patients with Shifts, % (n/N)*
Glucose Normal to High (<100 mg/dL to ≥126 mg/dL) | 12 (26/223) | 8 (18/219)
Impaired (≥100 mg/dL and <126 mg/dL) to High (≥126 mg/dL) | 24 (9/38) | 11 (5/47)
Increase ≥10 mg/dL | 66 (174/265) | 57 (154/270)
Hemoglobin A1c Normal (<5.7%) to Impaired (≥5.7% and <6.5%) | 42 (86/204) | 35 (68/197)
Normal to High (<5.7% to ≥6.5%) | 0.5 (1/204) | 1.5 (3/197)
Impaired (≥5.7% and <6.5%) to High (≥6.5%) | 9.5 (6/63) | 9.2 (7/76)
* n: number of patients with reported abnormal shifts; N: number of patients who had assessments at both baseline and endpoint for mean change, or normal at baseline and at least 1 post-baseline assessment for shift.

Dyslipidemia

In the 4-week, placebo-controlled trial in adult patients with schizophrenia, shifts in fasting triglycerides from normal to high occurred in 14% of patients treated with LYBALVI and 4% of patients treated with placebo.

In the 24-week olanzapine-controlled study, mean changes in fasting total cholesterol, LDL cholesterol, HDL cholesterol, and triglycerides were similar in patients treated with LYBALVI and in patients treated with olanzapine.

Weight Gain

In the 4-week placebo-controlled study in adult patients with schizophrenia, mean changes in weight, and proportion of patients with ≥7% weight increase, were greater in patients treated with LYBALVI and olanzapine than in patients on placebo. In that study, mean weight gain was 3.0 kg in patients treated with LYBALVI, 2.4 kg in patients treated with olanzapine, and 0.2 kg in patients treated with placebo. The proportion of patients with ≥7% weight increase was 26% in patients treated with LYBALVI, 20% in patients treated with olanzapine, and 5% in patients treated with placebo.

In the 24-week trial, LYBALVI-treated patients gained on average 4.2% of baseline body weight. The proportion of patients treated with LYBALVI with ≥10% body weight gain was 17.8% [see Clinical Studies (14)].

Extrapyramidal Symptoms

In the 4-week placebo-controlled trial in adult patients with schizophrenia, patients were assessed using the Simpson-Angus Rating Scale (SAS) for extrapyramidal symptoms (EPS) (total score ranges from 1 to 14), the Barnes Akathisia Rating Scale (BARS) for akathisia (total score ranges from 0 to 14), and the Abnormal Involuntary Movement Scale (AIMS) for dyskinesias (total score ranges from 0 to 28). The mean changes from baseline to last study visit for the SAS, BARS, and AIMS was similar in LYBALVI-treated patients and in placebo-treated patients. The mean changes for LYBALVI- vs placebo-treated patients were 0.00 vs -0.2 for AIMS, 0.0 vs -0.1 for BARS, and 0.0 vs -0.3 for SAS, respectively. The rate of parkinsonism (SAS total score >3) was lower in patients treated with LYBALVI (4%) compared to those on placebo (10%). The rates of akathisia (BARS global clinical assessment score ≥2) and dyskinesia (AIMS score ≥3 on any of the first 7 items, or a score ≥2 on two or more of any of the first 7 items) were similar in patients treated with LYBALVI and in those on placebo. Rates of akathisia were 6.0% and 8.2% in patients treated with LYBALVI and placebo, respectively, and the rate of dyskinesia was 1.5% both in LYBALVI-treated and in placebo-treated patients.

The frequency of reported adverse reactions related to extrapyramidal symptoms, including akathisia, restlessness, muscle spasms, bradykinesia, tremor, extrapyramidal disorder, and parkinsonism was 2% both in LYBALVI-treated and in placebo-treated patients.

In the 24-week active-controlled trial, the mean change from baseline to the last visit for the SAS, BARS, and AIMS was similar in LYBALVI-treated patients and in those treated with the active control. Extrapyramidal adverse reactions, including parkinsonism, akathisia, and dyskinesia, had a similar incidence in LYBALVI-treated patients and in those treated with the active control: any extrapyramidal symptom was 8%, akathisia was 3%.

Dystonia

Symptoms of dystonia, (prolonged abnormal contractions of muscle groups) may occur in susceptible individuals during the first few days of treatment. Dystonic symptoms include: spasm of the neck muscles, sometimes progressing to tightness of the throat, swallowing difficulty, difficulty breathing, and/or protrusion of the tongue. Although these symptoms can occur at low doses, they occur more frequently and with greater severity with high potency and at higher doses of first-generation antipsychotic drugs. An elevated risk of acute dystonia is observed in males and younger age groups.

Adverse Reactions in Patients with Bipolar Disorder

The safety of LYBALVI for the treatment of bipolar I disorder (mixed or manic) monotherapy and adjunct to lithium or valproate relies on information from adequate and well-controlled studies of olanzapine tablets in bipolar I disorder.

The most common adverse reactions (incidence of at least 5% of patients exposed to olanzapine and greater than or equal to twice the rate of placebo) from short-term trials of olanzapine (manic or mixed episodes) are somnolence, dry mouth, dizziness, asthenia, constipation, dyspepsia, increased appetite, and tremor.

The most common adverse reactions (incidence of at least 5% of patients exposed to olanzapine and greater than or equal to twice the rate of placebo) from short-term trials of olanzapine as adjunct to lithium or valproate (manic or mixed episodes) are dry mouth, weight gain, increased appetite, dizziness, back pain, constipation, speech disorder, increased salivation, amnesia, paresthesia.

6.2 Postmarketing Experience

The following adverse reactions have been identified during post-approval use of olanzapine. Because these reactions are reported voluntarily from a population of uncertain size, it is difficult to reliably estimate their frequency or evaluate a causal relationship to drug exposure.

- allergic reactions (e.g., anaphylactoid reaction, angioedema, pruritus or urticaria)
- cholestatic or mixed liver injury, hepatitis, jaundice
- diabetic coma, diabetic ketoacidosis
- discontinuation reaction (diaphoresis, nausea or vomiting)
- Drug reaction with eosinophilia and systemic symptoms (DRESS)
- fecal incontinence
- hyperlipidemia (random cholesterol levels of ≥240 mg/dL and random triglyceride levels of ≥1000 mg/dL have been reported)
- neutropenia
- pancreatitis
- priapism
- rash
- restless legs syndrome
- rhabdomyolysis
- salivary hypersecretion
- syndrome of inappropriate antidiuretic hormone secretion (SIADH)
- somnambulism
- stuttering [Stuttering was only studied in oral and long acting injection (LAI) formulations.]
- venous thromboembolic events (including pulmonary embolism and deep venous thrombosis)

7 DRUG INTERACTIONS

7.1 Effects of Other Drugs on LYBALVI

Table 4 describes clinically significant drug interactions where the concomitant use of other drugs affects LYBALVI.

Table 4: Effects of Other Drugs on LYBALVI
Strong CYP3A4 Inducer
Clinical Implication: | Coadministration of LYBALVI with a strong CYP3A4 inducer decreases AUCinf of olanzapine and samidorphan [see Clinical Pharmacology (12.3)], which may reduce LYBALVI efficacy.
Prevention or Management: | Concomitant use of LYBALVI with strong CYP3A4 inducers is not recommended.
Strong CYP1A2 Inhibitor
Clinical Implication: | Concomitant use of LYBALVI with a strong CYP1A2 inhibitor increases olanzapine AUC and Cmax [see Clinical Pharmacology (12.3)], which may increase the risk of LYBALVI adverse reactions.
Prevention or Management: | Consider reducing the dosage of the olanzapine component in LYBALVI when used concomitantly with strong CYP1A2 inhibitors.
CYP1A2 Inducer
Clinical Implication: | Concomitant use of LYBALVI with CYP1A2 inducers decreases olanzapine exposure [see Clinical Pharmacology (12.3)], which may reduce LYBALVI efficacy.
Prevention or Management: | Consider increasing the dosage of the olanzapine component in LYBALVI when used concomitantly with CYP1A2 inducers.
Diazepam, Alcohol, and Other CNS Acting Drugs
Clinical Implication: | Concomitant use of diazepam, alcohol, or other CNS acting drugs with LYBALVI may potentiate the orthostatic hypotension observed with olanzapine [see Warnings and Precautions (5.9)].
Prevention or Management: | LYBALVI should be used with caution in patients receiving concomitantly diazepam or other CNS acting drugs, or using alcohol.
Anticholinergic Drugs
Clinical Implication: | Concomitant treatment with olanzapine and other drugs with anticholinergic activity can increase the risk for severe gastrointestinal adverse reactions related to hypomotility.
Prevention or Management: | LYBALVI should be used with caution in patients receiving medications having anticholinergic (antimuscarinic) effects [see Warnings and Precautions (5.16)].

7.2 Effects of LYBALVI on Other Drugs

Table 5 describes clinically significant drug interactions where concomitant use of LYBALVI affects other drugs.

Table 5: Effects of LYBALVI on Other Drugs
Antihypertensive Agents
Clinical Implication: | LYBALVI may enhance the effects of certain antihypertensive agents.
Prevention or Management: | Monitor blood pressure and reduce dosage of antihypertensive drug in accordance with its approved product labeling.
Levodopa and Dopamine Agonists
Clinical Implication: | LYBALVI may antagonize the effects of levodopa and dopamine agonists.
Prevention or Management: | Concomitant use of LYBALVI is not recommended with levodopa and dopamine agonists.

7.3 Opioids

LYBALVI is contraindicated in patients who are using opioids or undergoing acute opioid withdrawal [see Contraindications (4)].

LYBALVI increases the risk of precipitating acute opioid withdrawal in patients who are dependent on opioids. Prior to initiating LYBALVI, there should be at least a 7-day opioid-free interval from the last use of short-acting opioids, and at least a 14-day opioid-free interval from the last use of long-acting opioids [see Dosage and Administration (2.1), Warnings and Precautions (5.3)].

In emergency situations, if a LYBALVI-treated patient requires opioid treatment for anesthesia or analgesia, discontinue LYBALVI. The opioid should be administered by properly trained individual(s), and the patient should be properly monitored in a setting equipped and staffed for cardiopulmonary resuscitation [see Warnings and Precautions (5.4)].

In non-emergency situations, if a LYBALVI-treated patient is expected to require opioid treatment (e.g., for analgesia during or after an elective surgical procedure) discontinue LYBALVI at least 5 days before opioid treatment and start olanzapine or another antipsychotic, if needed.

Given that LYBALVI contains samidorphan, an opioid antagonist, opioid treatment may be less effective or ineffective shortly after LYBALVI discontinuation because of the presence of samidorphan.

7.4 Interference with Laboratory Tests

Interference with Laboratory Tests for Opioid Detection

Because LYBALVI contains samidorphan, an opioid antagonist, LYBALVI may be cross-reactive with urinary immunoassay methods used for detecting opioids, resulting in false positive results. Use an alternative analytical technique (e.g., chromatographic methods) to confirm positive opioid urine drug screen results [see Contraindications (4) and Warnings and Precautions (5.19)].

8 USE IN SPECIFIC POPULATIONS

8.1 Pregnancy

Pregnancy Exposure Registry

There is a pregnancy exposure registry that monitors pregnancy outcomes in women exposed to atypical antipsychotics, including LYBALVI, during pregnancy. Healthcare providers are encouraged to register patients by contacting the National Pregnancy Registry for Atypical Antipsychotics at 1-866-961-2388 or visit https://womensmentalhealth.org/research/pregnancyregistry/atypicalantipsychotic/.

Risk Summary

Neonates exposed to antipsychotic drugs, including the olanzapine component of LYBALVI, during the third trimester are at risk for extrapyramidal and/or withdrawal symptoms following delivery (see Clinical Considerations). Overall published epidemiologic studies of pregnant women exposed to olanzapine have not established a drug-associated risk of major birth defects, miscarriage, or adverse maternal or fetal outcomes (see Data). There are no available data on the use of samidorphan or the combination of olanzapine and samidorphan in pregnant women to determine a drug-associated risk of major birth defects, miscarriage or adverse maternal or fetal outcomes. There are risks to the mother associated with untreated schizophrenia or bipolar I disorder and with exposure to antipsychotics, including LYBALVI, during pregnancy (see Clinical Considerations).

LYBALVI

In an animal reproduction study, oral administration of olanzapine and samidorphan to pregnant rats during the period of organogenesis produced adverse effects on embryofetal development and fetal toxicity at maternally toxic doses that are 6 times and >400 times the maximum recommended human dose (MRHD) of 20 mg/10 mg olanzapine/samidorphan in LYBALVI, respectively based on AUC. There were no adverse effects on embryofetal development at doses of olanzapine and samidorphan that are approximately 1 and 80 times, respectively, the MRHD based on AUC (see Data).

Olanzapine

In animal reproduction studies, there was no evidence of malformations in rats or rabbits when orally administered olanzapine at doses up to 9 and 30 times the MRHD dose (20 mg) based on mg/m^2 body surface area, respectively. In an oral rat embryofetal developmental toxicity study, early resorptions and increased numbers of nonviable fetuses were observed at a dose 9 times the MRHD based on mg/m^2 body surface area and gestation was prolonged at 5 times the MRHD based on mg/m^2 body surface area. In an oral rabbit embryofetal developmental toxicity study, fetal toxicity (manifested as increased resorptions and decreased fetal weight) occurred at a maternally toxic dose of olanzapine which is 30 times the MRHD based on mg/m^2 body surface area (see Data).

Samidorphan

In animal reproduction studies, oral administration of samidorphan to pregnant rats and rabbits during the period of organogenesis caused fetal toxicities in rats only at maternally toxic doses that are >248 times the human exposure at the MRHD of 10 mg/day based on AUC. Oral administration of samidorphan to pregnant rats during pregnancy and lactation resulted in lower pup survival and decreased pup weights at 188 times the human exposure at the MRHD based on AUC (see Data).

The estimated background risk of major birth defects and miscarriage for the indicated populations is unknown. All pregnancies have a background risk of birth defect, loss, or other adverse outcomes. In the U.S. general population, the estimated background risk of major birth defects and miscarriage in clinically recognized pregnancies is 2 to 4% and 15 to 20%, respectively.

Clinical Considerations

Disease-Associated Maternal and/or Embryofetal Risk

There is risk to the mother from untreated schizophrenia or bipolar I disorder, including increased risk of relapse, hospitalization and suicide. Schizophrenia and bipolar I disorder are associated with increased adverse perinatal outcomes, including preterm birth. It is not known if this is a direct result of the illness or other comorbid factors.

Fetal/ Neonatal Risks

Extrapyramidal and/or withdrawal symptoms, including agitation, hypertonia, hypotonia, tremor, somnolence, respiratory distress and feeding disorder have been reported in neonates who were exposed to antipsychotic drugs, including the olanzapine component of LYBALVI, during the third trimester of pregnancy. These symptoms have varied in severity. Monitor neonates for extrapyramidal and/or withdrawal symptoms and manage symptoms appropriately. Some neonates recovered within hours or days without specific treatment; others required prolonged hospitalization.

Data

Human Data

Published data from observational studies, birth registries, and case reports on the use of atypical antipsychotics during pregnancy do not report a clear association with antipsychotics and major birth defects. A retrospective cohort study from a Medicaid database of 9258 women exposed to antipsychotics during pregnancy did not indicate an overall increased risk for major birth defects.

Animal Data

LYBALVI

Olanzapine and samidorphan were orally administered to pregnant rats during the period of organogenesis at doses of 0.5/10, 2/50, 6/200, and 0/200 mg/kg/day (olanzapine/samidorphan) which are approximately <1/10 times to 6/448 times the MRHD of 20 mg/10 mg, olanzapine/samidorphan, respectively, based on AUC. Maternal toxicity consisting of decreased body weight and food consumption was observed at all dose levels. Administration of samidorphan alone (200 mg/kg/day) and 6/200 mg/kg/day olanzapine/samidorphan decreased mean fetal body weights, increased litter incidence of bent ribs and bent scapula; however, the incidence of bent scapula and bent ribs was not increased when samidorphan was administered in combination with olanzapine compared to the incidence with samidorphan alone. Administration of olanzapine/samidorphan at 6/200 mg/kg/day also increased resorptions and post-implantation loss, with correlating lower mean viable fetuses and litter size. The no observed adverse effect level (NOAEL) for embryofetal development is 2/50 mg/kg/day, which is approximately 1/80 times the MRHD of 20 mg/10 mg olanzapine/samidorphan respectively, based on AUC.

Olanzapine

Olanzapine was orally administered to pregnant rats and rabbits during the period of organogenesis at doses up to 18 mg/kg/day in rats and at doses up to 30 mg/kg/day in rabbits (9 times and 30 times the MRHD of 20 mg/day based on mg/m^2 body surface area, respectively), and no evidence of malformations was observed. In an oral rat embryofetal developmental toxicity study, early resorptions and increased numbers of nonviable fetuses were observed at a dose of 18 mg/kg/day (9 times the MRHD based on mg/m^2 body surface area). Gestation was prolonged at 10 mg/kg/day (5 times the MRHD based on mg/m^2 body surface area). In an oral rabbit embryofetal developmental toxicity study, fetal toxicity (manifested as increased resorptions and decreased fetal weight) occurred at a maternally toxic dose of olanzapine at 30 mg/kg/day (30 times the MRHD based on mg/m^2 body surface area).

Samidorphan

Samidorphan was orally administered to pregnant rats during the period of organogenesis at doses of 25, 100, and 300 mg/kg/day, which are approximately 29 to 742 times the MRHD of 10 mg/day based on AUC. Samidorphan was associated with an increased incidence of skeletal variations (unossified sternebrae and bent ribs) at maternally toxic doses of ≥100 mg/kg/day, and skeletal malformations (bent or misshapen forelimbs, hindlimbs, and/or scapula) at 300 mg/kg/day which are >248 and 742 times the MRHD based on AUC, respectively. The NOAEL for embryofetal development is 25 mg/kg/day, which is approximately 29 times the MRHD based on AUC.

Samidorphan did not cause adverse effects on embryofetal development when orally administered to pregnant rabbits during the period of organogenesis at doses of 10, 30, and 90 mg/kg/day, which are up to approximately 143 times the MRHD based on AUC.

Samidorphan was orally administered to pregnant rats during pregnancy and lactation at doses of 10, 30, or 100 mg/kg/day, which are approximately 7 to 188 times the MRHD based on AUC. Reduced pup survival, lower birth weights, and decreased pup body weight gains were observed at 100 mg/kg/day, which is 188 times the MRHD based on AUC. The NOAEL of 30 mg/kg/day is approximately 36 times the MRHD based on AUC. There were no adverse effects on pup developmental landmarks, learning, memory, reflexes, or fertility.

8.2 Lactation

Risk Summary

Olanzapine and samidorphan are present in human milk. A clinical lactation study in 12 healthy lactating women demonstrated that olanzapine and samidorphan are present in low levels in human milk (see Data). However, there are reports of excess sedation, irritability, poor feeding and extrapyramidal symptoms (tremors and abnormal muscle movements) in infants exposed to olanzapine through breast milk (see Clinical Considerations). There are no data on the effects of samidorphan or the combination of olanzapine and samidorphan on the breastfed infant, or on milk production.

The developmental and health benefits of breastfeeding should be considered along with the mother's clinical need for LYBALVI and any potential adverse effects on the breastfed infant from LYBALVI or from the underlying maternal condition.

Clinical Considerations

Infants exposed to LYBALVI should be monitored for excess sedation, irritability, poor feeding and extrapyramidal symptoms (tremors and abnormal muscle movements).

Data

A single dose milk-only lactation study was conducted in 12 healthy adult lactating women. Following a 5 mg/10 mg oral dose of olanzapine and samidorphan, the mean quantities in human milk were detected to be 0.002 mg and 0.006 mg, respectively. The calculated weight-adjusted infant daily oral dose for olanzapine (~ 0.0005 mg/kg) and samidorphan (0.001 mg/kg) was less than 1% of the weight-adjusted maternal dose for olanzapine (0.07 mg/kg) and samidorphan (0.15 mg/kg), respectively.

8.3 Females and Males of Reproductive Potential

Infertility

Females

Based on the pharmacologic action of olanzapine (D2 antagonism), treatment with LYBALVI may result in an increase in serum prolactin levels, which may lead to a reversible reduction in fertility in females of reproductive potential [see Warnings and Precautions (5.17)].

8.4 Pediatric Use

The safety and effectiveness of LYBALVI have not been established in pediatric patients.

8.5 Geriatric Use

Clinical studies of LYBALVI did not include sufficient numbers of patients 65 years of age and older to determine whether they responded differently than younger adult patients.

Olanzapine

Of the 2,500 patients in premarketing clinical studies with orally administered olanzapine, 11% (263) were 65 years of age or over. Elderly patients with dementia-related psychosis treated with antipsychotic drugs are at an increased risk of death. LYBALVI is not approved for the treatment of patients with dementia-related psychosis [see Dosage and Administration (2.5), Warnings and Precautions (5.1)].

Studies in elderly patients with dementia-related psychosis have suggested that there may be a different tolerability profile in this population compared to younger patients with schizophrenia. Elderly patients with dementia-related psychosis treated with olanzapine are at an increased risk of death compared to placebo.

- In placebo-controlled studies of olanzapine in elderly patients with dementia-related psychosis, there was a higher incidence of cerebrovascular adverse events (e.g., stroke, transient ischemic attack) in patients treated with olanzapine, compared to patients treated with placebo.
- In five placebo-controlled studies of olanzapine in elderly patients with dementia-related psychosis (n=1,184), the following adverse reactions were reported in olanzapine-treated patients at an incidence of at least 2% and significantly greater than in placebo-treated patients: falls, somnolence, peripheral edema, abnormal gait, urinary incontinence, lethargy, increased weight, asthenia, pyrexia, pneumonia, dry mouth and visual hallucinations. The rate of discontinuation due to adverse reactions was greater with olanzapine than with placebo (13% vs 7%).

Consider a lower dosage of the olanzapine component of LYBALVI in geriatric patients who may have decreased clearance or an exaggerated pharmacodynamic response to olanzapine (e.g., oversedation) [see Dosage and Administration (2.5)].

8.6 Hepatic Impairment

Olanzapine and samidorphan plasma exposures were found to be higher in subjects with moderate hepatic impairment than in subjects with normal hepatic function. The effect of severe hepatic impairment was not studied. The higher plasma exposure in patients with moderate hepatic impairment was not expected to be clinically relevant. No dose adjustment of LYBALVI is needed in patients with hepatic impairment [see Clinical Pharmacology (12.3)].

8.7 Renal Impairment

Plasma exposure to olanzapine and samidorphan was higher in patients with severe renal impairment (eGFR 15 to 29 mL/minute/1.73 m^2) compared to those with normal renal function [see Clinical Pharmacology (12.3)]. No dose adjustment of LYBALVI is needed in patients with mild (eGFR 60 to 89 mL/minute/1.73 m^2), moderate (eGFR 30 to 59 mL/minute/1.73 m^2), or severe renal impairment (eGFR 15 to 29 mL/minute/1.73 m^2).

The effect of LYBALVI in patients with end-stage renal disease was not studied. LYBALVI is not recommended for patients with end-stage renal disease (eGFR of <15 mL/minute/1.73 m^2).

10 OVERDOSAGE

Human Experience

There is limited clinical experience with overdose with LYBALVI. In premarketing clinical trials of LYBALVI involving 861 patients, overdose of LYBALVI was identified in 7 patients. This included 4 patients with accidental overdose, 2 with intentional overdose, and 1 due to a medication administration error. None of the reported overdoses was associated with a fatal outcome. There was a reported ingestion of 11 tablets of LYBALVI 10 mg/10 mg (5.5 times and 11 times the maximum recommended daily dosage of the olanzapine and samidorphan components of LYBALVI, respectively). The patient was found unresponsive and admitted to the hospital. Medical treatment included fluids, electrolytes, a diuretic, and a detoxicant; the patient stabilized within 2 days.

In postmarketing reports of overdose with olanzapine, a component of LYBALVI, symptoms included agitation/aggressiveness, dysarthria, tachycardia, various extrapyramidal symptoms, and reduced level of consciousness ranging from sedation to coma. Less commonly reported symptoms include: aspiration, cardiopulmonary arrest, cardiac arrhythmias (such as supraventricular tachycardia and 1 patient experiencing sinus pause with spontaneous resumption of normal rhythm), delirium, possible neuroleptic malignant syndrome, respiratory depression/arrest, convulsion, hypertension, and hypotension. In 1 case of death, the amount of acutely ingested olanzapine was reported to be possibly as low as 450 mg; however, in another case, a patient was reported to survive an acute olanzapine ingestion of approximately 2,000 mg.

Management of Overdose

No specific antidotes for LYBALVI are known. In managing overdose, provide supportive care, including close medical supervision and monitoring, and consider the possibility of multiple drug involvement. If an overdose occurs, consult a certified Poison Control Center (1-800-222-1222) for additional overdosage management recommendations.

11 DESCRIPTION

LYBALVI is a combination of olanzapine, an atypical antipsychotic, and samidorphan (as samidorphan L-malate), an opioid antagonist.

Olanzapine is 2-methyl-4-(4-methyl-1-piperazinyl)-10H-thieno[2,3-b][1,5]benzodiazepine. The molecular formula of olanzapine is: C17H20N4S and the molecular weight is 312.44 g/mol. It is a yellow crystalline powder and has pKa values of 7.80 and 5.44. The chemical structure is:

Samidorphan L-malate is morphinan-3-carboxamide, 17-(cyclopropylmethyl)-4, 14-dihydroxy-6-oxo-, (2S)-2-hydroxybutanedioate. The molecular formula of samidorphan L-malate is C21H26N2O4 • C4H6O5 and the molecular weight is 504.54 g/mol. It is a white to off-white crystalline powder and has pKa values of 8.3 (amine) and 10.1 (phenol). The chemical structure is:

LYBALVI is intended for oral administration and is available as film-coated, bilayer tablets in the following strengths: 5 mg/10 mg, 10 mg/10 mg, 15 mg/10 mg, and 20 mg/10 mg of olanzapine and samidorphan (equivalent to 13.6 mg of samidorphan L-malate).

Inactive ingredients include colloidal silicon dioxide, crospovidone, lactose monohydrate, magnesium stearate, and microcrystalline cellulose. The film coating ingredients include hypromellose, titanium dioxide, triacetin, and color additives [iron oxide yellow (5 mg/10 mg); iron oxide yellow and iron oxide red (10 mg/10 mg); FD&C Blue No. 2/ indigo carmine aluminum lake (15 mg/10 mg); iron oxide red (20 mg/10 mg)].

12 CLINICAL PHARMACOLOGY

12.1 Mechanism of Action

The mechanism of action of olanzapine is unclear; however, its efficacy in the treatment of schizophrenia or bipolar I disorder could be mediated through a combination of dopamine and serotonin type 2 (5HT2) antagonism.

The mechanism of action of samidorphan could be mediated through opioid receptor antagonism.

12.2 Pharmacodynamics

Olanzapine

Olanzapine binds with high affinity to the following receptors: serotonin 5HT2A/2C, 5HT6 (Ki=4, 11, and 5 nM, respectively), dopamine D1-4 (Ki=11–31 nM), histamine H1 (Ki=7 nM), and adrenergic α1 receptors (Ki=19 nM). Olanzapine is an antagonist with moderate affinity binding for serotonin 5HT3 (Ki=57 nM) and muscarinic M1-5 (Ki=73, 96, 132, 32, and 48 nM, respectively). Olanzapine binds with low affinity to GABAA, BZD, and β-adrenergic receptors (Ki>10 μM).

Samidorphan

Samidorphan binds to the mu-, kappa-, and delta-opioid receptors (Ki=0.052, 0.23, and 2.7 nM, respectively). Samidorphan is an antagonist at the mu-opioid receptors with partial agonist activity at kappa- and delta-opioid receptors.

The N-dealkylated major human metabolite binds to the mu-, kappa-, and delta-opioid receptors (Ki=0.26, 23, and 56 nM, respectively), and functions as a mu-opioid receptor agonist. The N-oxide major human metabolite binds to mu-, kappa-, and delta-opioid receptors (Ki=8, 110, and 280 nM, respectively) and functions as a mu-opioid receptor antagonist.

Cardiac Electrophysiology

At doses up to 30 mg/30 mg (1.5 times and 3 times the maximum recommended daily dosage of olanzapine and samidorphan, respectively), LYBALVI does not prolong QTc interval to any clinically relevant extent.

12.3 Pharmacokinetics

The pharmacokinetics of both olanzapine and samidorphan are linear over the clinical dose range and there is no PK interaction between olanzapine and samidorphan after oral administration of LYBALVI. Steady-state concentrations of olanzapine and samidorphan are reached within 7 days of commencement of once-daily administration of LYBALVI. The primary pharmacological activities of LYBALVI are due to the parent drugs, olanzapine and samidorphan.

Following a single dose administration of LYBALVI (10 mg olanzapine/10 mg samidorphan), the mean AUC0-inf and Cmax of olanzapine was 628 ng·h/mL and 16 ng/mL, respectively. The mean AUC0-inf and Cmax of olanzapine after 10 mg single dose administration of olanzapine tablet was 610 ng·h/mL and 16 ng/mL, respectively.

Pharmacokinetic properties of the components of LYBALVI are provided in Table 6.

Table 6: Pharmacokinetic Properties of the Components of LYBALVI
Parameters | Olanzapine | Samidorphan
General
Steady State Exposure (20 mg olanzapine/10 mg samidorphan)
Cmax (ng/mL)a | 64.6 (28.9) | 45.1 (11.4)
AUC24h (ng∙hr/mL)a | 1086 (556) | 364 (112)
Time to Reach Steady State | 7 days | 5 days
Accumulation at Steady State | 2-fold | 1.3-fold
Absorption
Absolute Oral Bioavailability | NA | 69%
Tmax (h)b | 4.5–7 | 1–2
Effect of Food
Cmax Ratioc | 0.88 (0.82, 0.95) | 0.85 (0.76, 0.94)
AUC Ratioc | 0.93 (0.91, 0.96) | 1.03 (1.00, 1.05)
Distribution
Plasma Protein Binding | 93% | 23% - 33%
Blood-to-Plasma Ratio | Not Determined | 0.8
Elimination
t1/2 (h)d | 35–52 | 7–11
CL/F (L/h)d | 15–22 | 35–45
Metabolism
Primary Pathway(s) | UGT1A4, CYP1A2 | CYP3A4
Minor Pathway(s) | CYP2D6 | CYP3A5, CYP2C19, CYP2C8
Major Circulating Metabolites | 10-N-glucuronide and 4′-N-desmethyl-olanzapine. Both metabolites lack pharmacological activity at the therapeutic concentrations | N-dealkylated and cis-N-oxide metabolites. Neither metabolite contributes to the pharmacological effects of samidorphan
Excretion
Primary Route of Elimination | Metabolism | Metabolism
Urine (Unchanged) | 7% | 18%
Urine (Unchanged + metabolites) | 57% | 67%
Feces (Unchanged + metabolites) | 30% | 16%
Abbreviations: AUC24h=area under the concentration-time curve over the 24-hour dosing interval; Cmax=maximum plasma concentration; CYP=cytochrome P450; NA=not applicable; Tmax=time to Cmax; t½=terminal elimination half-life; UGT=Uridine 5'-diphospho-glucuronosyltransferase.
a Presented as arithmetic mean (standard deviation).
b Presented as range of the median across multiple studies.
c Geometric mean ratio (90% confidence interval) [high fat meal/fasting]. High fat meal defined as meal containing approximately 900-1000 calories and 50% fat content. No clinically relevant food effect.
d Presented as range of the mean across multiple studies.

Specific Populations

Geriatric Patients

The pharmacokinetics of olanzapine may be altered in geriatric patients [see Dosage and Administration (2.5), Use in Specific Populations (8.5)]. In a study involving 24 healthy subjects, the mean elimination half-life of olanzapine was about 1.5 times greater in elderly subjects (≥65 years) than in non-elderly subjects (<65 years).

No effect of age on samidorphan pharmacokinetics was found in a study involving 12 elderly [aged 66-80 years old (6 male, 6 female)] and 24 young [aged 18-39 years old (12 male, 12 female)] healthy subjects administered a single oral dose of 10 mg samidorphan.

Male and Female Patients

Clearance of olanzapine is approximately 30% lower in females than males. In clinical trials, however, there were no apparent differences between males and females in efficacy or adverse reactions. In clinical studies and population pharmacokinetic analysis, LYBALVI pharmacokinetics were consistent with that of olanzapine (as monotherapy) with no apparent effect of sex on samidorphan pharmacokinetics.

Racial or Ethnic Groups

In vivo studies of olanzapine as monotherapy have shown that olanzapine exposures are similar among Japanese, Chinese, and Caucasians, especially after normalization for body weight difference. A population pharmacokinetic analysis found that the clearance of olanzapine is greater in Black subjects (N=255) than non-Black subjects (N=329 White and N=17 other races), and that samidorphan pharmacokinetics are not affected by race.

Patients with Hepatic and Renal Impairment

Effects of hepatic and renal impairment on the exposure of olanzapine and samidorphan are summarized in Figure 1.

Figure 1: Effects of Hepatic Impairment and Renal Impairment on Olanzapine and Samidorphan Pharmacokinetics

* Based on PBPK simulations, the predicted Cmax and AUC ratios for samidorphan in subjects with severe hepatic impairment relative to healthy subjects were 2.1 and 2.3, respectively.

Smoking Status

Olanzapine clearance was approximately 40% higher in smokers than in non-smokers. Samidorphan pharmacokinetics were not affected by smoking.

Combined Effects

The combined effects of age, smoking, and sex could lead to substantial difference in olanzapine pharmacokinetics. The clearance of olanzapine in young smoking males, for example, may be 3 times higher than that in elderly nonsmoking females. Population pharmacokinetic analysis indicated that samidorphan pharmacokinetics was not affected by age, sex, race, and smoking status.

Drug Interaction Studies

Effect of Other Drugs on LYBALVI

Coadministration of LYBALVI with rifampin, a strong CYP3A4 inducer, decreased the total systemic exposure (based on area under the concentration-time curve from time 0 extrapolated to infinity [AUCinf]) of olanzapine and samidorphan by 48% and 73%, respectively (Figure 2).

Fluvoxamine, a strong CYP1A2 inhibitor, decreases clearance of olanzapine. This results in a mean increase in olanzapine Cmax following fluvoxamine of 54% in female nonsmokers and 77% in male smokers. The mean increase in olanzapine AUC in female nonsmokers and male smokers is 52% and 108%, respectively.

Carbamazepine therapy (200 mg bid) causes an approximately 50% increased clearance of olanzapine. This increase is likely due to the fact that carbamazepine is a CYP1A2 inducer.

Based on PBPK simulations, Itraconazole, a strong CYP3A inhibitor, is predicted to increase samidorphan Cmax by 25% and AUC by 56%.

Figure 2: Effect of Other Drugs on LYBALVI

Effect of LYBALVI on Other Drugs

Coadministration of LYBALVI and lithium or valproate did not have a clinically significant effect on the PK of lithium or valproate (Figure 3). Based on these results, no dosage adjustment of lithium or valproate is necessary when coadministered with LYBALVI.

Figure 3: Effect of LYBALVI on Other Drugs

In vitro Studies

Cytochrome P450 (CYP) Enzymes: Olanzapine does not inhibit CYP1A2, CYP2C9, CYP2C19, CYP2D6, or CYP3A4/5. Samidorphan does not inhibit CYP1A2, CYP2B6, CYP2C8, CYP2C9, CYP2C19, CYP2D6, or CYP3A4/5. Samidorphan does not induce CYP1A2, CYP2B6, or CYP3A4/5.

Transporter Systems: Samidorphan is not a substrate of P-glycoprotein (P-gp; multidrug resistance protein 1), organic anion transporter (OATP) 1B1, or OATP1B3. Samidorphan does not inhibit these transporters or breast cancer resistance protein (BCRP), organic anion transporter (OAT)1, OAT3, or organic cation transporter (OCT)2.

13 NONCLINICAL TOXICOLOGY

13.1 Carcinogenesis, Mutagenesis, Impairment of Fertility

Carcinogenesis

Olanzapine

Oral carcinogenicity studies were conducted in mice and rats. Olanzapine was administered to mice in two 78-week studies at doses of 3, 10, 30/20 mg/kg/day (equivalent to 0.8 to 5 times the MRHD of 20 mg/day based on mg/m^2 body surface area) and 0.25, 2, 8 mg/kg/day (equivalent to 0.06 to 2 times the MRHD based on mg/m^2 body surface area). Rats were dosed for 2 years at doses of 0.25, 1, 2.5, 4 mg/kg/day (males) and 0.25, 1, 4, 8 mg/kg/day (females) (equivalent to 0.13 to 2 and 0.13 to 4 times the MRHD based on mg/m^2 body surface area, respectively). The incidence of liver hemangiomas and hemangiosarcomas was significantly increased in 1 mouse study in female mice dosed at 8 mg/kg/day (2 times the MRHD based on mg/m^2 body surface area). These tumors were not increased in another mouse study in females dosed at 10 or 30/20 mg/kg/day (2 to 5 times the MRHD based on mg/m^2 body surface area); in this study, there was a high incidence of early mortalities in males of the 30/20 mg/kg/day group. The incidence of mammary gland adenomas and adenocarcinomas was significantly increased in female mice dosed at ≥2 mg/kg/day and in female rats dosed at ≥4 mg/kg/day (0.5 and 2 times the MRHD based on mg/m^2 body surface area, respectively). Antipsychotic drugs have been shown to chronically elevate prolactin levels in rodents. Serum prolactin levels were not measured during the olanzapine carcinogenicity studies; however, measurements during subchronic toxicity studies showed that olanzapine elevated serum prolactin levels up to 4-fold in rats at the same doses used in the carcinogenicity study. An increase in mammary gland neoplasms has been found in rodents after chronic administration of other antipsychotic drugs and is considered to be prolactin mediated. The relevance for human risk of the finding of prolactin mediated endocrine tumors in rodents is unknown [see Warnings and Precautions (5.17)].

Samidorphan

Samidorphan did not increase the incidence of tumors in rats administered oral doses of 20, 35, or 75 mg/kg/day (males) and 15, 30, or 60 mg/kg/day (females) for 96 (males) and 95 (females) weeks, which are up to 32 and 237 times the MRHD of 10 mg/day in males and females, respectively based on AUC. Samidorphan did not increase the incidence of tumors in transgenic rasH2 mice administered oral doses of 125, 250, or 500 mg/kg/day for 26 weeks.

Mutagenesis

Olanzapine

No evidence of genotoxic potential for olanzapine was found in the Ames reverse mutation test, in vivo micronucleus test in mice, the chromosome aberration test in Chinese hamster ovary cells, unscheduled DNA synthesis test in rat hepatocytes, induction of forward mutation test in mouse lymphoma cells, or in vivo sister chromatid exchange test in bone marrow of Chinese hamsters.

Samidorphan

No evidence of genotoxicity of samidorphan was found in the in vitro Ames bacterial reverse mutation test, the in vitro chromosome aberration assay in human peripheral blood lymphocytes or in the in vivo mouse bone marrow micronucleus assay.

Impairment of Fertility

Olanzapine

In an oral fertility and reproductive performance study in rats, male mating performance, but not fertility, was impaired at a dose of 22.4 mg/kg/day and female fertility was decreased at a dose of 3 mg/kg/day (11 and 1.5 times the MRHD of 20 mg/day based on mg/m^2 body surface area, respectively). Discontinuance of olanzapine treatment reversed the effects on male mating performance. In female rats, the precoital period was increased and the mating index reduced at 5 mg/kg/day (2.5 times the MRHD based on mg/m^2 body surface area). Diestrus was prolonged and estrus delayed at 1.1 mg/kg/day (0.6 times the daily oral MRHD based on mg/m^2 body surface area); therefore, olanzapine may produce a delay in ovulation.

Samidorphan

Samidorphan did not impair fertility when administered orally to female rats at doses of 30, 150, or 450 mg/kg/day prior to and throughout mating and continuing to gestation day 7. The doses are approximately 32, 297, and >680 times the MRHD of 10 mg/day based on AUC, respectively. However, estrous cycle lengths were increased, and the total number of estrous cycles were decreased in females at the highest dose of 450 mg/kg/day. Samidorphan did not affect fertility when orally administered to male rats at doses of 10, 30, or 100 mg/kg/day prior to and throughout mating; the highest dose is approximately 16 times the MRHD based on AUC.

13.2 Animal Toxicology and/or Pharmacology

Olanzapine

In animal studies with olanzapine, the principal hematologic findings were reversible peripheral cytopenia in individual dogs dosed at 10 mg/kg (17 times the MRHD of 20 mg olanzapine based on mg/m^2 body surface area), dose-related decreases in lymphocytes and neutrophils in mice, and lymphopenia in rats. A few dogs treated with 10 mg/kg developed reversible neutropenia and/or reversible hemolytic anemia between 1 and 10 months of treatment. Dose-related decreases in lymphocytes and neutrophils were seen in mice given doses of 10 mg/kg (equal to 2 times the MRHD based on mg/m^2 body surface area) in studies of 3 months' duration. Nonspecific lymphopenia, consistent with decreased body weight gain, occurred in rats receiving 22.5 mg/kg (11 times the MRHD based on mg/m^2 body surface area) for 3 months or 16 mg/kg (8 times the MRHD based on mg/m^2 body surface area) for 6 or 12 months. No evidence of bone marrow cytotoxicity was found in any of the species examined. Bone marrows were normocellular or hypercellular, indicating that the reductions in circulating blood cells were probably due to peripheral (non-marrow) factors.

14 CLINICAL STUDIES

14.1 Schizophrenia

The efficacy of LYBALVI in the treatment of schizophrenia in adults is based, in part, upon adequate and well-controlled studies of orally administered olanzapine. Efficacy of LYBALVI was also evaluated in a 4-week, randomized, double-blind, placebo- and active-controlled study (Study 1).

In Study 1 (NCT02634346), adult patients who met DSM-5 criteria for schizophrenia were randomized in a 1:1:1 ratio to LYBALVI, olanzapine, or placebo for 4 weeks of daily dosing. Dosing was flexible based on clinical response and tolerability for the first 2 weeks of the study; doses thereafter were fixed. Patients assigned to LYBALVI could receive either 10 mg/10 mg or 20 mg/10 mg, and patients assigned to olanzapine could receive either 10 mg or 20 mg. The study was designed to compare LYBALVI with placebo, not with olanzapine.

Eligible patients were 18 to 70 years of age, with a body mass index (BMI) of 18.0–40.0 kg/m^2, Positive and Negative Syndrome Scale (PANSS) total score of ≥80, and a score of ≥4 on at least 3 of the selected Positive Scale items. Patients were also required to have a Clinical Global Impression-Severity (CGI-S) score ≥4.

The primary efficacy endpoint was change from baseline in PANSS total score at Week 4. The PANSS is a 30-item scale that measures positive symptoms of schizophrenia (7 items), negative symptoms of schizophrenia (7 items), and general psychopathology (16 items), each rated on a scale of 1 (absent) to 7 (extreme). Total PANSS scores range from 30 to 210, with a higher score reflecting greater symptom severity. The secondary efficacy endpoint was defined as the change from baseline in CGI-S score at Week 4. The CGI-S is a validated scale that requires clinicians to rate a patient's current illness severity and overall clinical state based on experience with the illness population. Scores range from 1 (normal, not at all ill) to 7 (extremely ill).

Compared with patients on placebo, a statistically significant improvement in the change from baseline in PANSS total score at Week 4 was observed in patients treated with LYBALVI (Table 7). The inclusion of samidorphan in LYBALVI did not appear to negatively impact the antipsychotic efficacy of olanzapine.

Table 7: Primary Efficacy Results for Change from Baseline in PANSS Total Score at Week 4 in Patients with Schizophrenia (Study 1)
Treatment Group | Total PANSS Score
Treatment Group | Baseline Mean Score (SD) | LS Mean Change from Baseline (SE) | Placebo-subtracted Differencea (95% CI)
LYBALVI (10 mg/10 mg, 20 mg/10 mg) (N=132) | 101.8 (11.6) | -23.9 (1.3) | -6.4 (-10.0, -2.8)
Placebo (N=133) | 102.7 (11.9) | -17.5 (1.3) | --
Olanzapine (10 mg, 20 mg) (N=132) | 100.6 (12.1) | -22.8 (1.3) | -5.3 (-8.9, -1.7)
Abbreviations: CI: confidence interval; LS: least squares; SD: standard deviation; SE: standard error.
a Difference (drug minus placebo) in least squares mean change from baseline. A negative value for the placebo subtracted difference represents improvement.

The change from baseline in PANSS total score in Study 1 is displayed in Figure 4.

Figure 4: Change from Baseline in PANSS Total Score by Time (Week) in Patients with Schizophrenia (Study 1)

Error bars represent standard error. The numbers under the figure indicate the number of patients at each timepoint.

Compared with patients on placebo, a statistically significant improvement in CGI-S score at Week 4 was observed in patients treated with LYBALVI.

Evaluation of Weight Changes in Patients with Schizophrenia

In Study 2 (NCT02694328), adult patients who met DSM-5 criteria for schizophrenia were randomized in a 1:1 ratio to LYBALVI or olanzapine for 24 weeks of daily dosing. Dosing was flexible for the first 4 weeks of the study, and doses were fixed thereafter. Patients were treated with doses of LYBALVI of 10 mg/10 mg or 20 mg/10 mg, or with doses of olanzapine of 10 mg or 20 mg.

Eligible patients were 18 to 55 years of age with a body mass index (BMI) of 18 to 30 kg/m^2, PANSS total score of 50 to 90, CGI-S score of ≤4, and symptoms suitable for outpatient treatment; patients with diabetes mellitus were excluded.

The proportions of patients who discontinued study drug in the 24-week trial was 36% for both the LYBALVI and olanzapine-treated groups.

Weight Gain

The co-primary endpoints were percent change from baseline in body weight and the proportion of patients who gained ≥10% body weight at Week 24. LYBALVI was compared to olanzapine for each co-primary endpoint [see Adverse Reactions (6)]. Patients on stable, chronic olanzapine therapy were not specifically studied, so the weight effect of switching from olanzapine to LYBALVI is unknown.

Treatment with LYBALVI was associated with statistically significantly less weight gain than treatment with olanzapine, and with a smaller proportion of patients who gained ≥10% body weight (Table 8). Figure 5 displays the percent change in body weight over time.

Table 8: Primary Efficacy Results for Change from Baseline in Weight at Week 24 in Patients with Schizophrenia (Study 2)
Treatment Group | % Change From Baseline in Body Weight |  |  | ≥10% Body Weight Gain
Treatment Group |  | Baseline Mean, kg (SD) | LS Mean % Change From Baseline (SE) | Olanzapine-subtracted Difference (95% CI) | Percentage of Patients | Olanzapine-subtracted Risk Difference (95% CI)
LYBALVI (10 mg/10 mg, 20 mg/10 mg) (N=266) | 77.0 (13.7) | 4.2 (0.7) | -2.4 (-3.9, -0.9) | 17.8 | -13.7 (-22.8, -4.6)
Olanzapine (10 mg, 20 mg) (N=272) | 77.5 (13.5) | 6.6 (0.7) | __ | 29.8 | __
Abbreviations: CI: confidence interval; LS: least squares; SD: standard deviation; SE: standard error.

Figure 5: Percent Change from Baseline in Body Weight by Time (Week) in Patients with Schizophrenia (Study 2)

Error bars represent standard error. The numbers under the figure indicate the number of patients at each timepoint.

14.2 Bipolar I Disorder

The efficacy of LYBALVI in the treatment of adult patients with bipolar I disorder has been established based on adequate and well-controlled studies of orally administered olanzapine. The information below describes the results of adequate and well-controlled studies of olanzapine in patients with bipolar I disorder.

Monotherapy

The efficacy of oral olanzapine in the treatment of manic or mixed episodes was established in 2 short-term (one 3-week and one 4-week) placebo-controlled studies in adult patients who met the DSM-IV criteria for bipolar I disorder with manic or mixed episodes. These studies included patients with or without psychotic features and with or without a rapid-cycling course.

The primary rating instrument used for assessing manic symptoms in these studies was the Young Mania Rating Scale (Y-MRS), an 11-item clinician-rated scale traditionally used to assess the degree of manic symptomatology in a range from 0 (no manic features) to 60 (maximum score). The primary outcome in these studies was change from baseline in the Y-MRS total score. The results of the studies follow:

In one 3-week placebo-controlled study (n=67) which involved a dose range of olanzapine (5 mg/day to 20 mg/day, once daily, starting at 10 mg/day), olanzapine was superior to placebo in the reduction of Y-MRS total score. In an identically designed study conducted simultaneously with the first study olanzapine demonstrated a similar treatment difference but, possibly due to sample size and site variability, was not shown to be superior to placebo on this outcome.

In a 4-week placebo-controlled study (n=115) which involved a dose range of olanzapine (5 mg/day to 20 mg/day, once daily, starting at 15 mg/day), olanzapine was superior to placebo in the reduction of Y-MRS total score.

In another study, 361 patients meeting DSM-IV criteria for a manic or mixed episode of bipolar I disorder who had responded during an initial open-label treatment phase for about 2 weeks, on average, to olanzapine 5 mg/day to 20 mg/day were randomized to either continuation of olanzapine at their same dose (n=225) or to placebo (n=136), for observation of relapse. Approximately 50% of the patients had discontinued from the olanzapine group by day 59 and 50% of the placebo group had discontinued by day 23 of double-blind treatment. Response during the open-label phase was defined by having a decrease of the Y-MRS total score to ≤12 and HAM-D 21 to ≤8. Relapse during the double-blind phase was defined as an increase of the Y-MRS or HAM-D 21 total score to ≥15, or being hospitalized for either mania or depression. In the randomized phase, patients receiving continued olanzapine experienced a significantly longer time to relapse.

Adjunct to Lithium or Valproate

The efficacy of oral olanzapine with concomitant lithium or valproate in the treatment of manic or mixed episodes was established in 2 controlled studies in patients who met the DSM-IV criteria for bipolar I disorder with manic or mixed episodes. These studies included patients with or without psychotic features and with or without a rapid-cycling course. The results of the studies follow:

In one 6-week placebo-controlled combination study, 175 outpatients on lithium or valproate therapy with inadequately controlled manic or mixed symptoms (Y-MRS ≥16) were randomized to receive either olanzapine or placebo, in combination with their original therapy. Olanzapine (in a dose range of 5 mg/day to 20 mg/day, once daily, starting at 10 mg/day) combined with lithium or valproate (in a therapeutic range of 0.6 mEq/L to 1.2 mEq/L or 50 μg/mL to 125 μg/mL, respectively) was superior to lithium or valproate alone in the reduction of Y-MRS total score.

In a second 6-week placebo-controlled combination study, 169 outpatients on lithium or valproate therapy with inadequately controlled manic or mixed symptoms (Y-MRS ≥16) were randomized to receive either olanzapine or placebo, in combination with their original therapy. Olanzapine (in a dose range of 5 mg/day to 20 mg/day, once daily, starting at 10 mg/day) combined with lithium or valproate (in a therapeutic range of 0.6 mEq/L to 1.2 mEq/L or 50 μg/mL to 125 μg/mL, respectively) was superior to lithium or valproate alone in the reduction of Y-MRS total score.

16 HOW SUPPLIED/ STORAGE AND HANDLING

How Supplied

LYBALVI (olanzapine and samidorphan) tablets have markings on both sides and are available as described in Table 9.

Table 9: LYBALVI Tablet Presentations
Tablet Strength(s) (olanzapine/samidorphan) | Tablet Description | Package Configuration | NDC Number
5 mg/10 mg | Yellow, capsule-shaped, debossed with “OS” on one side and “5” on the other side | 30-count bottle with child resistant closure | 65757-651-42
10 mg/10 mg | Orange, capsule-shaped, debossed with “OS” on one side and “10” on the other side | 30-count bottle with child resistant closure | 65757-652-42
15 mg/10 mg | Blue, capsule-shaped, debossed with “OS” on one side and “15” on the other side | 30-count bottle with child resistant closure | 65757-653-42
20 mg/10 mg | Pink, capsule-shaped, debossed with “OS” on one side and “20” on the other side | 30-count bottle with child resistant closure | 65757-654-42

Storage and Handling

Store at room temperature 20°C to 25°C (68°F to 77°F) with excursions permitted between 15°C and 30°C (59°F and 86°F) [see USP Controlled Room Temperature].

Keep tightly closed and protect from moisture.

17 PATIENT COUNSELING INFORMATION

Advise the patient to read the FDA-approved patient labeling (Medication Guide).

Concomitant Use with Opioids is Contraindicated

Advise patients to inform their healthcare provider if they are taking, or plan to take any opioids for any reason, as LYBALVI is contraindicated with use of opioids or those undergoing acute opioid withdrawal [see Dosage and Administration (2.1), Contraindications (4), Warnings and Precautions (5.3), Drug Interactions (7.3)].

Precipitation of Opioid Withdrawal

Advise patients not to take LYBALVI when using opioids because of the risks of opioid withdrawal syndrome, sometimes requiring hospitalization. Advise patients that they should have an opioid-free period of a minimum of 7 days after last use of short-acting opioids and 14 days from last use of long-acting opioids before initiating LYBALVI [see Contraindications (4), Warnings and Precautions (5.3)].

Risk of Opioid Overdosage

Advise patients that they may be at increased risk of opioid overdosage if they attempt to use high or repeated opioid doses. Inform patients of the potential consequences of trying to overcome the opioid blockade and the serious risks of taking opioids concurrently with LYBALVI or while transitioning off LYBALVI [see Warnings and Precautions (5.4)].

Risk of Resuming Opioids in Patients with Prior Opioid Use

Advise patients that if they used opioids prior to LYBALVI treatment, they may have decreased opioid tolerance if they use opioids after LYBALVI discontinuation or interruption [see Warnings and Precautions (5.4)].

Neuroleptic Malignant Syndrome

Counsel patients about a potentially fatal adverse reaction, Neuroleptic Malignant Syndrome (NMS), that has been reported with administration of antipsychotic drugs. Advise patients, family members, or caregivers to contact the healthcare provider or to report to the emergency room if they experience signs and symptoms of NMS [see Warnings and Precautions (5.5)].

Drug Reaction with Eosinophilia and Systemic Symptoms

Advise patients to report to their health care provider at the earliest onset of any signs and symptoms that may be associated with Drug Reaction with Eosinophilia and Systemic Symptoms (DRESS) [see Warnings and Precautions (5.6)].

Metabolic Changes

Educate patients about the risk of metabolic changes, how to recognize symptoms of hyperglycemia and diabetes mellitus, and the need for specific monitoring, including blood glucose, lipids, and weight [see Warnings and Precautions (5.7)].

Tardive Dyskinesia

Counsel patients on the signs and symptoms of tardive dyskinesia and to contact their healthcare provider if these abnormal movements occur [see Warnings and Precautions (5.8)].

Orthostatic Hypotension and Syncope

Educate patients about the risk of orthostatic hypotension and syncope, especially early in treatment, and also at times of re-initiating treatment [see Warnings and Precautions (5.9), Drug Interactions (7.2)].

Leukopenia/Neutropenia

Advise patients with a pre-existing low WBC or a history of drug induced leukopenia/ neutropenia that they should have their CBC monitored while taking LYBALVI [see Warnings and Precautions (5.11)].

Potential for Cognitive and Motor Impairment

Caution patients about performing activities requiring mental alertness, such as operating hazardous machinery or operating a motor vehicle, until they are reasonably certain that LYBALVI therapy does not affect them adversely [see Warnings and Precautions (5.14)].

Concomitant Medication

Advise patients to inform their healthcare providers if they are taking, or plan to take any other olanzapine containing medication. Advise patients to inform their healthcare providers of any changes to their current prescription or over-the-counter medications because there is a potential for interactions [see Drug Interactions (7.1, 7.2, 7.3)].

Body Temperature Dysregulation

Educate patients regarding appropriate care in avoiding overheating and dehydration [see Warnings and Precautions (5.15)].

Alcohol

Advise patients to use caution consuming alcohol while taking LYBALVI [see Drug Interactions (7.1)].

Pregnancy

Advise patients to notify their healthcare provider if they become pregnant or intend to become pregnant during treatment with LYBALVI. Advise patients that LYBALVI used during the third trimester may cause extrapyramidal and/or withdrawal symptoms (agitation, hypertonia, hypotonia, tremor, somnolence, respiratory distress, and feeding disorder) in a neonate. Advise patients that there is a pregnancy exposure registry that monitors pregnancy outcomes in women exposed to LYBALVI during pregnancy [see Use in Specific Populations (8.1)].

Lactation

Advise breastfeeding women using LYBALVI to monitor infants for excess sedation, irritability, poor feeding, and extrapyramidal symptoms (tremors and abnormal muscle movements) and to seek medical care if they notice these signs [see Use in Specific Populations (8.2)].

Infertility

Advise females of reproductive potential that LYBALVI may impair fertility due to an increase in serum prolactin levels. The effects on fertility are reversible [see Use in Specific Populations (8.3)].

Administration Information

Advise patients to take LYBALVI once daily and not split or combine tablets [see Dosage and Administration (2.4)].

Distributed by:
Alkermes, Inc.
Waltham, MA 02451

©2026 Alkermes, Inc. All rights reserved.

ALKERMES® is a registered trademark of Alkermes, Inc. LYBALVI® is a registered trademark of Alkermes Pharma Ireland Limited, used by Alkermes, Inc., under license.

Printed in U.S.A.

MEDICATION GUIDE
LYBALVI® (lee bawl' vee)
(olanzapine and samidorphan)
tablets, for oral use

If your healthcare provider prescribes LYBALVI in combination with valproate or lithium, also read the Medication Guide that comes with those medicines.

What is the most important information I should know about LYBALVI?
LYBALVI may cause serious side effects, including:

- Increased risk of death in elderly people with dementia related psychosis. LYBALVI increases the risk of death in elderly people who have lost touch with reality (psychosis) due to confusion and memory loss (dementia). LYBALVI is not approved for the treatment of people with dementia-related psychosis.

What is LYBALVI?
LYBALVI is a prescription medicine which contains 2 medicines (olanzapine and samidorphan) used in adults:

- to treat schizophrenia
- alone for short-term (acute) or maintenance treatment of manic or mixed episodes that happen with bipolar I disorder
- in combination with valproate or lithium to treat manic or mixed episodes that happen with bipolar I disorder

It is not known if LYBALVI is safe or effective in children.

Do not take LYBALVI if you are taking opioids or are experiencing acute opioid withdrawal. See “What are the possible side effects of LYBALVI.”

Before taking LYBALVI, tell your healthcare provider about all of your medical conditions, including if you:

- have or had heart problems or a stroke
- use or abuse street (illegal) drugs
- have or had low or high blood pressure
- have kidney problems
- have diabetes or high blood sugar or a family history of diabetes or high blood sugar
- have or have had high levels of total cholesterol, LDL cholesterol, or triglycerides or low levels of HDL cholesterol
- have or had a low white blood cell count
- have problems swallowing
- have or had seizures (convulsions)
- have or had problems with urination or prostate problems
- have or had breast cancer
- have or had constipation or a bowel obstruction
- have or had high prolactin levels
- are pregnant or plan to become pregnant. Talk to your healthcare provider about the risks to you and your unborn or newborn baby if you take LYBALVI during pregnancy.
  - Tell your healthcare provider right away if you become pregnant or think you are pregnant during treatment with LYBALVI.
  - If you become pregnant during treatment with LYBALVI, talk to your healthcare provider about registering with the National Pregnancy Registry for Atypical Antipsychotics. You can register by calling 1-866-961-2388 or visit http://womensmentalhealth.org/clinical-and-research-programs/pregnancyregistry/
- are breastfeeding or plan to breastfeed. LYBALVI passes into your breast milk. Talk to your healthcare provider about the best way to feed your baby during treatment with LYBALVI.

Tell your healthcare provider about all the medicines you take, including prescription and over-the-counter medicines, vitamins, and herbal supplements.
LYBALVI and other medicines may affect each other causing possible serious side effects. LYBALVI may affect the way other medicines work, and other medicines may affect how LYBALVI works.
Especially tell your healthcare provider if you:

- take opioids or have stopped taking opioids in the past 14 days
- take or plan to take other olanzapine containing medicines

Your healthcare provider can tell you if it is safe to take LYBALVI with your other medicines. Do not start or stop any medicines while taking LYBALVI without first talking to your healthcare provider.
Tell your healthcare provider if you take a urine drug screening test because LYBALVI may affect your test results. Tell those giving the drug screening test that you are taking LYBALVI.
Know the medicines you take. Keep a list of your medicines to show your healthcare provider and pharmacist when you get a new medicine.

How should I take LYBALVI?

- Take LYBALVI exactly as your healthcare provider tells you to take it. Do not change the dose or stop taking LYBALVI without first talking to your healthcare provider.
- Take LYBALVI 1 time each day with or without food.
- Swallow LYBALVI tablets whole. Do not split or combine different strength LYBALVI tablets.
- If you take too much LYBALVI, call your Poison Control Center at 1-800-222-1222 or go to the nearest hospital emergency room right away.

What should I avoid while taking LYBALVI?

- Do not drive a car, operate machinery, or do other dangerous activities until you know how LYBALVI affects you. LYBALVI may make you feel drowsy.
- Avoid drinking alcohol during treatment with LYBALVI.
- Avoid getting over-heated or dehydrated.
  - Do not exercise too much.
  - In hot weather, stay inside in a cool place if possible.
  - Stay out of the sun. Do not wear too much clothing or heavy clothing.
  - Drink plenty of water.

What are the possible side effects of LYBALVI?
LYBALVI may cause serious side effects, including:

- See “What is the most important information I should know about LYBALVI?”
- Stroke (cerebrovascular problems) in elderly people with dementia-related psychosis that can lead to death.
- Opioid withdrawal. Do not take LYBALVI for at least 7 days after you stopped taking short-acting opioids and for at least 14 days after you stopped taking long-acting opioids. One of the medicines in LYBALVI (samidorphan) can cause opioid withdrawal that may be severe and cause hospitalization in people who are physically dependent on opioids. Talk to your healthcare provider if you have questions about the type of opioid you take.
- Risk of life-threatening opioid overdose. You should not start taking opioids for at least 5 days after you stop treatment with LYBALVI. One of the medicines in LYBALVI (samidorphan) can increase your chance of having an opioid overdose that can cause death if you take opioids during treatment or within 5 days after stopping treatment with LYBALVI.
  You can accidentally overdose in 2 ways:
  - LYBALVI blocks the effects of opioids, such as heroin, methadone, or opioid pain medicines. Do not take large amounts of opioids to try to overcome the opioid-blocking effects of LYBALVI. This can lead to serious injury, coma, or death.
  - After you take LYBALVI, its blocking effect slowly decreases and completely goes away over time. You may be more sensitive to the effects of opioids. If you have used opioid street drugs or opioid-containing medicines in the past, using opioids in amounts that you used before treatment with LYBALVI can lead to overdose or death.
  It is important that you tell your family and the people closest to you of this increased sensitivity to opioids and the risk of overdose.
  You or someone close to you should get emergency medical help right away if you:
  - have trouble breathing
  - become very drowsy with slowed breathing
  - have slow, shallow breathing (little chest movement with breathing)
  - feel faint, very dizzy, confused, or have unusual symptoms
  Tell your healthcare provider if you are taking LYBALVI before a medical procedure or surgery.
- Neuroleptic malignant syndrome (NMS), a serious condition that can lead to death. Call your healthcare provider or go to the nearest hospital emergency room right away if you have some or all of the following signs and symptoms of NMS:

- high fever
- stiff muscles
- confusion

- sweating
- changes in your breathing, pulse, heart rate, and blood pressure

- Drug Reaction with Eosinophilia and Systemic Symptoms (DRESS): One of the medicines in LYBALVI (olanzapine) can cause DRESS which can cause death. Tell your healthcare provider right away if you develop any of the following symptoms of DRESS, including:

- rash
- swollen glands
- liver problems
- heart problems

- fever
- kidney problems
- lung problems

- Problems with your metabolism such as:
  - high blood sugar (hyperglycemia) and diabetes. Increases in blood sugar can happen in some people who take LYBALVI. Extremely high blood sugar can lead to coma or death. Your healthcare provider should check your blood sugar before you start and regularly during treatment with LYBALVI.
    Call your healthcare provider if you have any of these symptoms of high blood sugar during treatment with LYBALVI:
    - feel very thirsty
    - feel very hungry
    - feel sick to your stomach
    - need to urinate more than usual
    - feel weak or tired
    - feel confused, or your breath smells fruity
  - increased fat levels (cholesterol and triglycerides) in your blood. Your healthcare provider should check the fat levels in your blood before you start and regularly during treatment with LYBALVI.
  - weight gain. You and your healthcare provider should check your weight before you start and often during treatment with LYBALVI.

- Uncontrolled body movements (tardive dyskinesia). LYBALVI may cause movements that you cannot control in your face, tongue, or other body parts. Tardive dyskinesia may not go away, even if you stop taking LYBALVI. Tardive dyskinesia may also start after you stop taking LYBALVI.
- Decreased blood pressure (orthostatic hypotension) and fainting. You may feel lightheaded or faint when you rise too quickly from a sitting or lying position.
- Falls. LYBALVI may make you sleepy or dizzy, may cause a decrease in your blood pressure when changing position (orthostatic hypotension), and can slow your thinking and motor skills which may lead to falls that can cause fractures or other injuries.
- Low white blood cell count. Your healthcare provider may do blood tests during the first few months of treatment with LYBALVI.
- Difficulty swallowing that can cause food or liquid to get into your lungs.
- Seizures (convulsions).
- Problems controlling your body temperature so that you feel too warm. See “What should I avoid while taking LYBALVI?”
- Increased prolactin levels in your blood. Your healthcare provider may do blood tests to check your prolactin levels during treatment with LYBALVI.

The most common side effects of LYBALVI when used to treat people with schizophrenia include:

- weight gain
- dry mouth

- sleepiness
- headache

The most common side effects of LYBALVI when used alone to treat people with mixed or manic episodes that happen with bipolar I disorder include:

- weakness
- constipation
- sleepiness
- shaking

- dry mouth
- increased appetite
- dizziness

The most common side effects of LYBALVI when used in combination with lithium or valproate to treat people with mixed or manic episodes that happen with bipolar I disorder include:

- dry mouth
- increased appetite
- back pain
- problems speaking
- memory problems

- weight gain
- dizziness
- constipation
- mouth watering
- numbness and tingling in your arm and legs

These are not all the possible side effects of LYBALVI.
Call your healthcare provider for medical advice about side effects. You may report side effects to FDA at 1-800-FDA-1088.

How should I store LYBALVI?

- Store LYBALVI at room temperature between 68°F to 77°F (20°C to 25°C).
- Keep tightly closed, in a dry place, and away from moisture.

Keep LYBALVI and all medicines out of the reach of children.

General information about the safe and effective use of LYBALVI
Medicines are sometimes prescribed for purposes other than those listed in a Medication Guide. Do not use LYBALVI for a condition for which it is not prescribed. Do not give LYBALVI to other people, even if they have the same symptoms that you have. It may harm them. You can ask your pharmacist or healthcare provider for information about LYBALVI that is written for healthcare providers.

What are the ingredients in LYBALVI?
Active ingredients: olanzapine and samidorphan
Inactive ingredients: colloidal silicon dioxide, crospovidone, lactose monohydrate, magnesium stearate and microcrystalline cellulose. The film coating ingredients include hypromellose, titanium dioxide, triacetin and iron oxide yellow (5 mg/10 mg); iron oxide yellow and iron oxide red (10 mg/10 mg); FD&C Blue No. 2/indigo carmine aluminum lake (15 mg/10 mg); iron oxide red (20 mg/10 mg)
Manufactured and marketed by: Alkermes, Inc., Waltham, MA 02451
For more information, go to www.LYBALVI.com or call 1-844-LYBALVI (1-844-592-2584).

This Medication Guide has been approved by the U.S. Food and Drug Administration

Revised: 1/2024

PACKAGE LABEL

Principal Display Panel - 5 mg/10 mg 30 Tablets Carton Label

NDC 65757-651-42 Rx Only

LYBALVI®

(olanzapine/samidorphan)
tablets

5 mg/10 mg

Dispense the accompanying
Medication Guide to each patient.

30 Tablets

PACKAGE LABEL

Principal Display Panel - 10 mg/10 mg 30 Tablets Carton Label

NDC 65757-652-42 Rx Only

LYBALVI®

(olanzapine/samidorphan)
tablets

10 mg/10 mg

Dispense the accompanying
Medication Guide to each patient.

30 Tablets

PACKAGE LABEL

Principal Display Panel - 15 mg/10 mg 30 Tablets Carton Label

NDC 65757-653-42 Rx Only

LYBALVI®

(olanzapine/samidorphan)
tablets

15 mg/10 mg

Dispense the accompanying
Medication Guide to each patient.

30 Tablets

PACKAGE LABEL

Principal Display Panel - 20 mg/10 mg 30 Tablets Carton Label

NDC 65757-654-42 Rx Only

LYBALVI®

(olanzapine/samidorphan)
tablets

20 mg/10 mg

Dispense the accompanying
Medication Guide to each patient.

30 Tablets